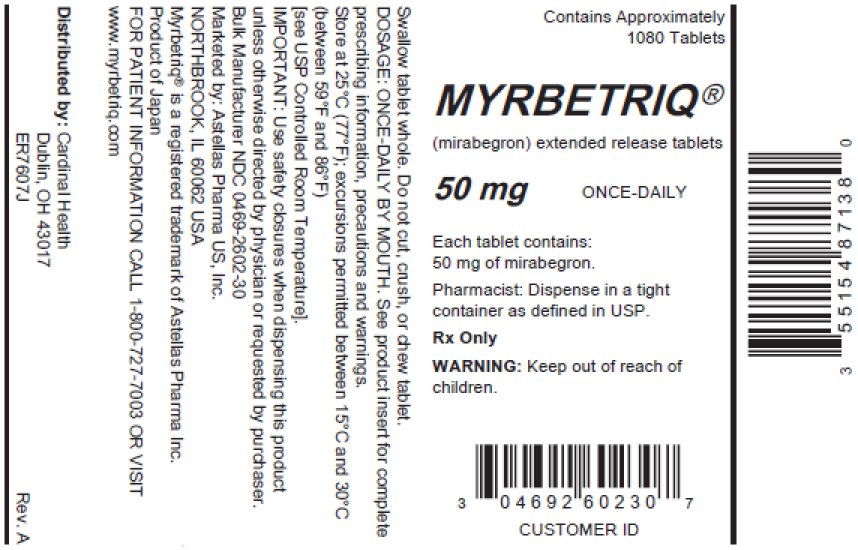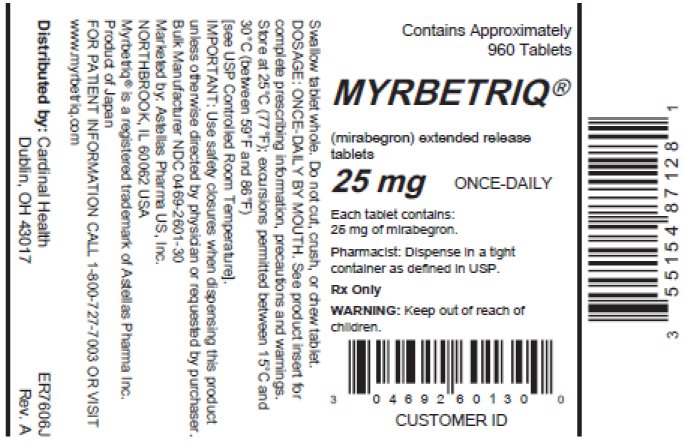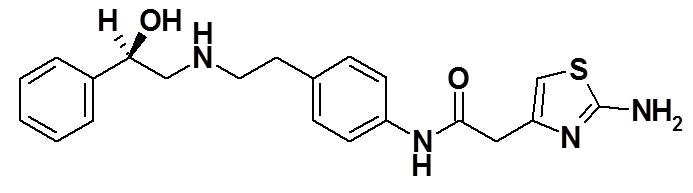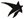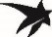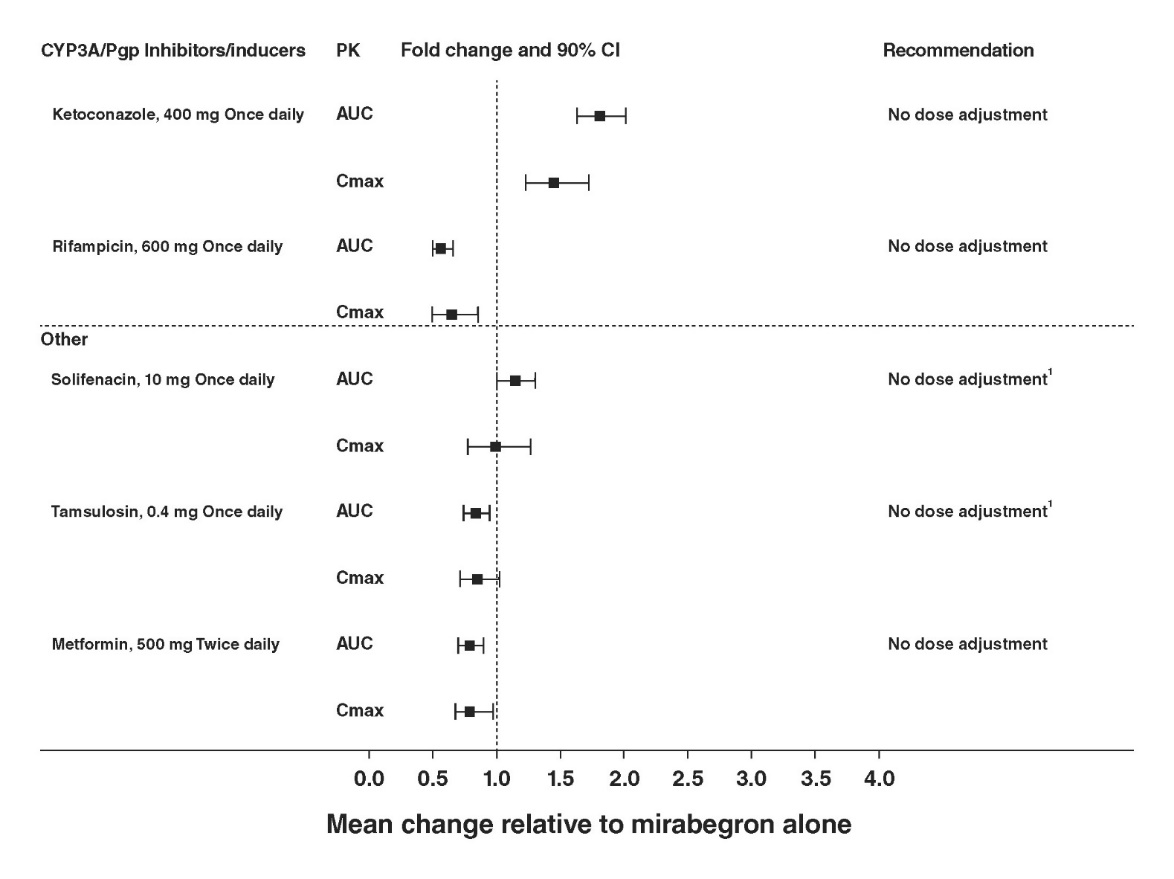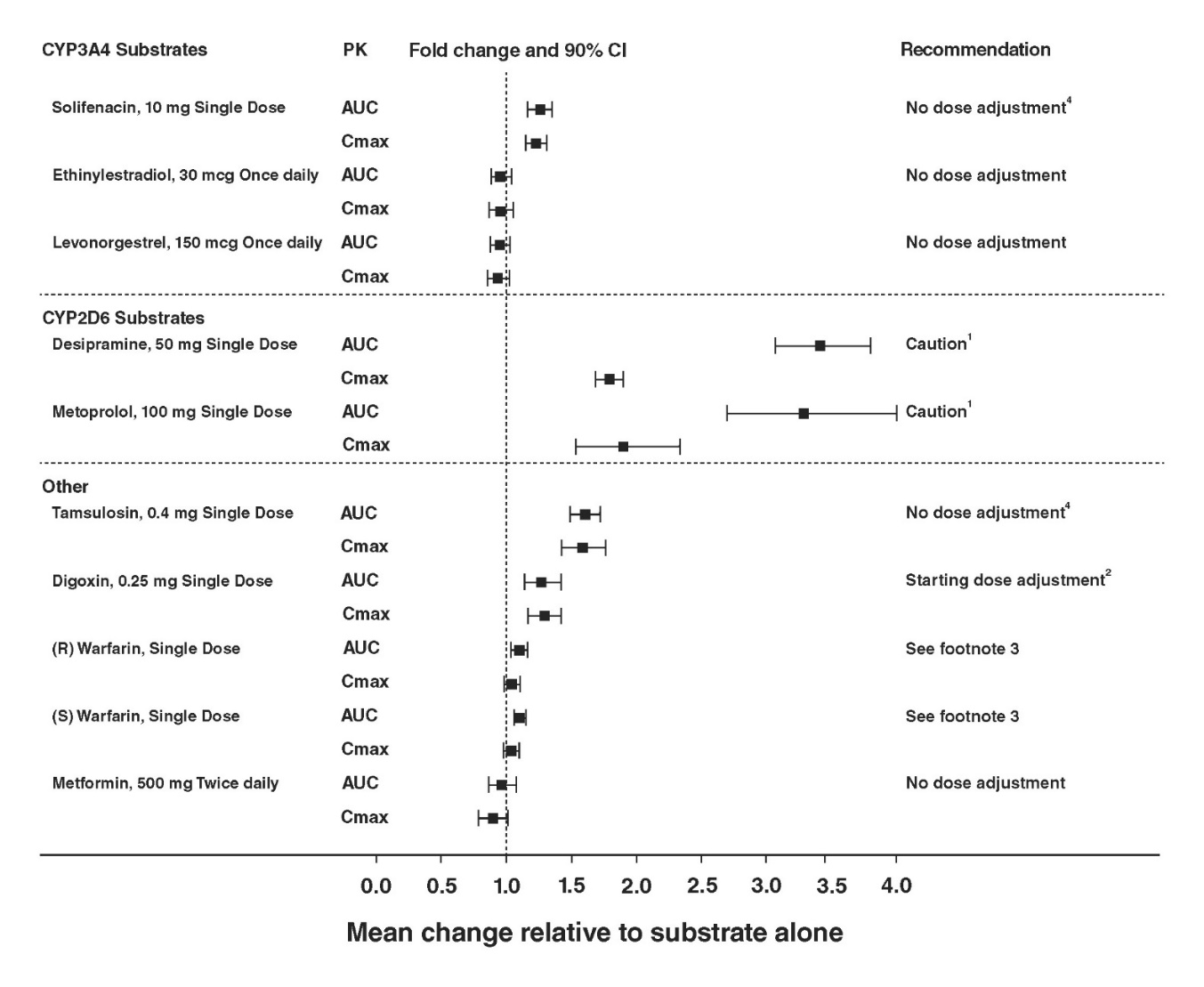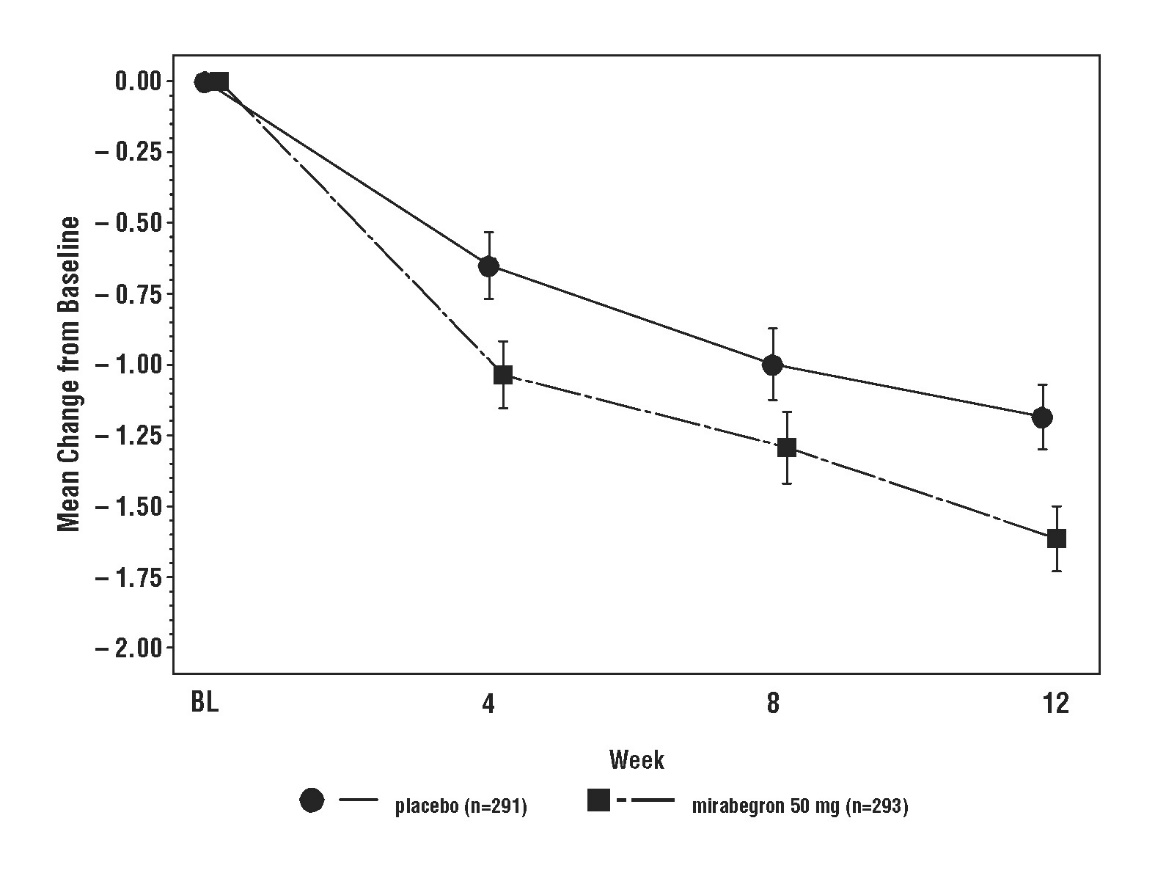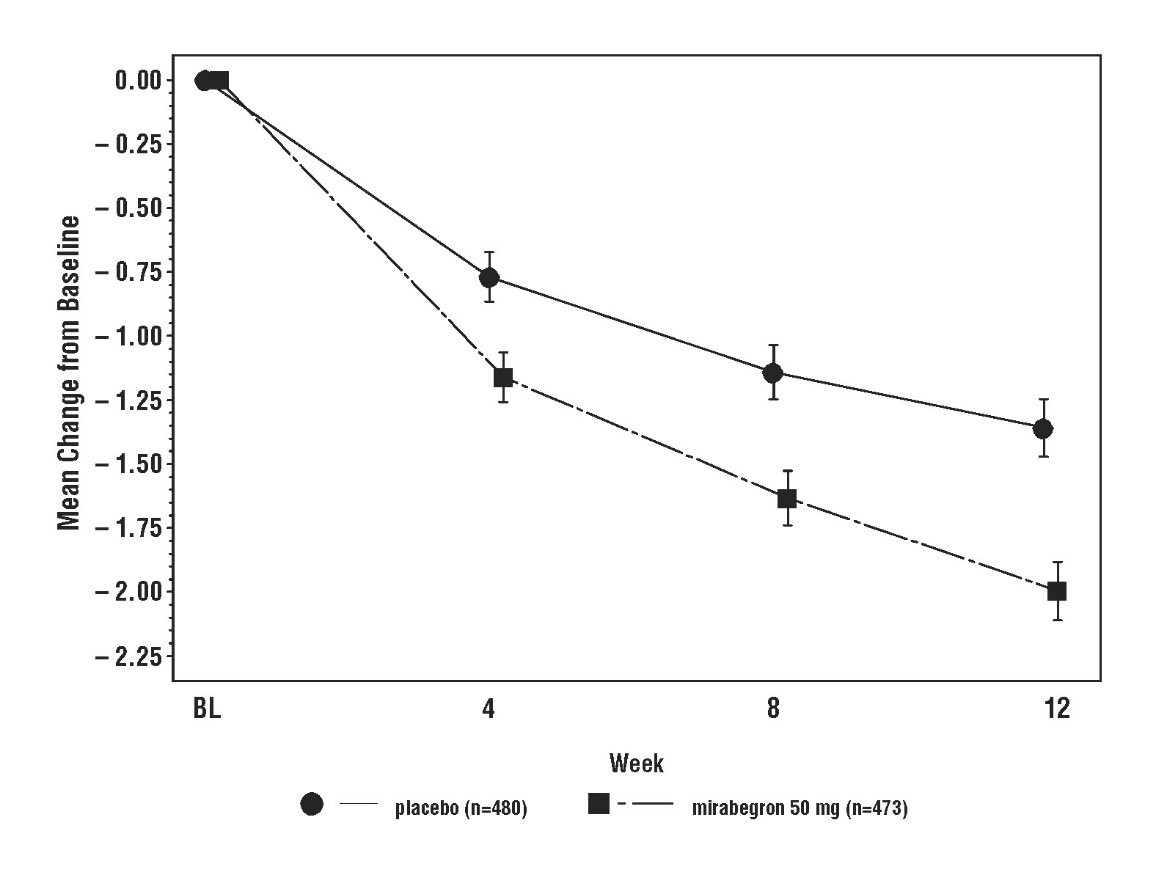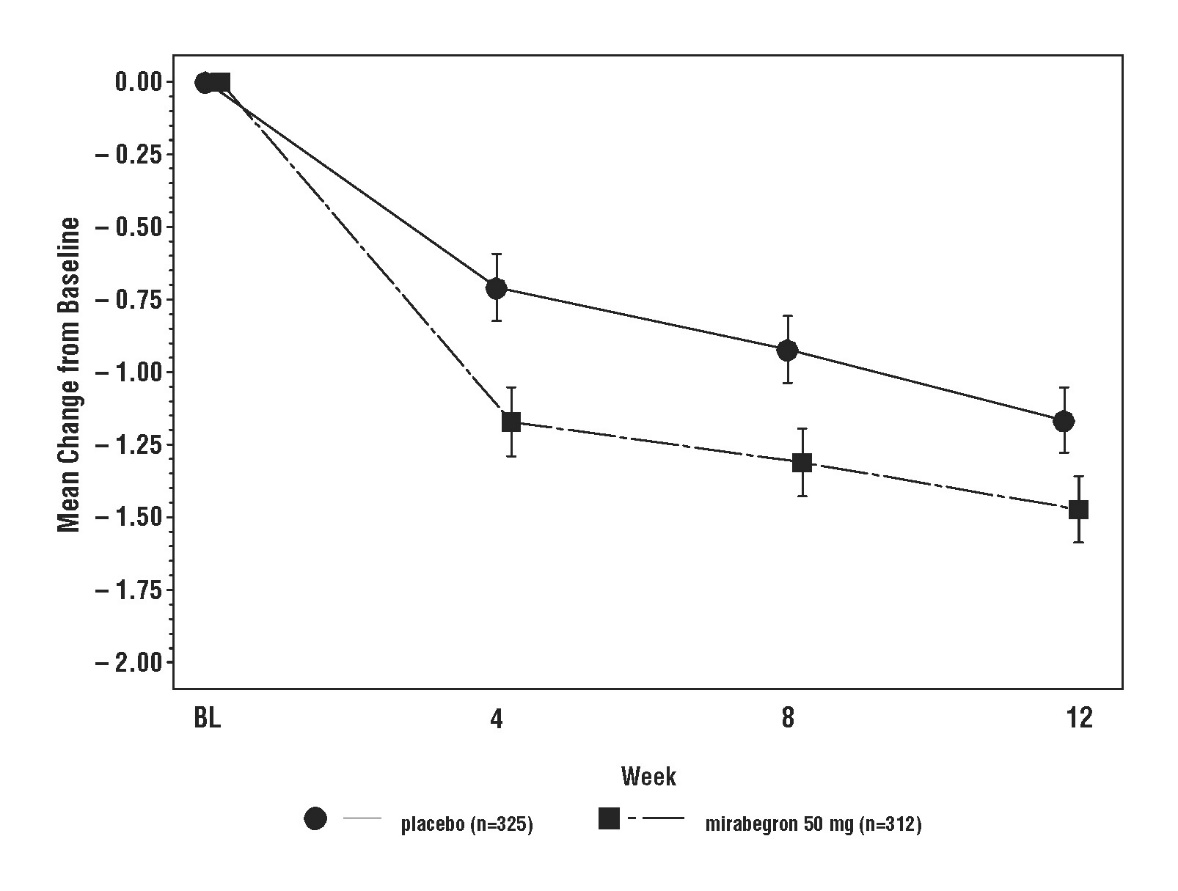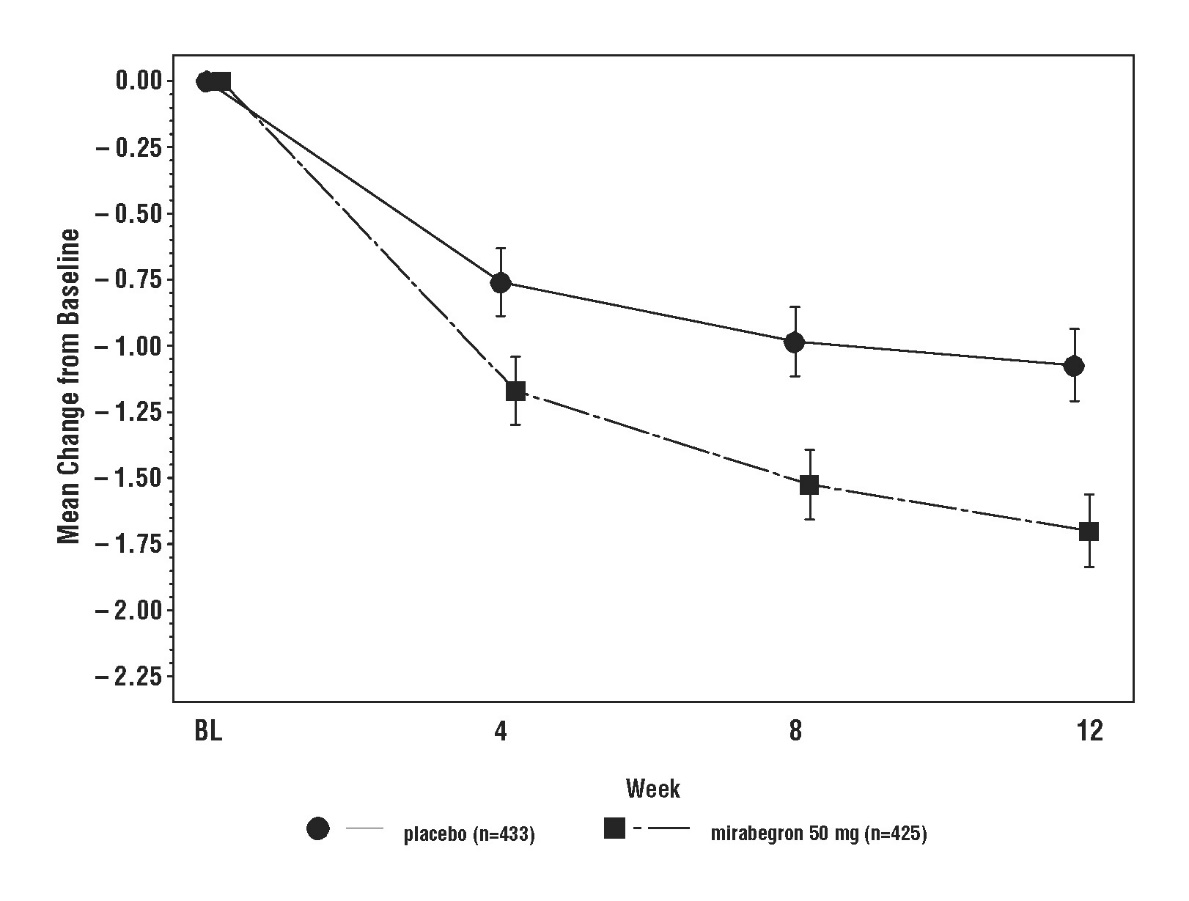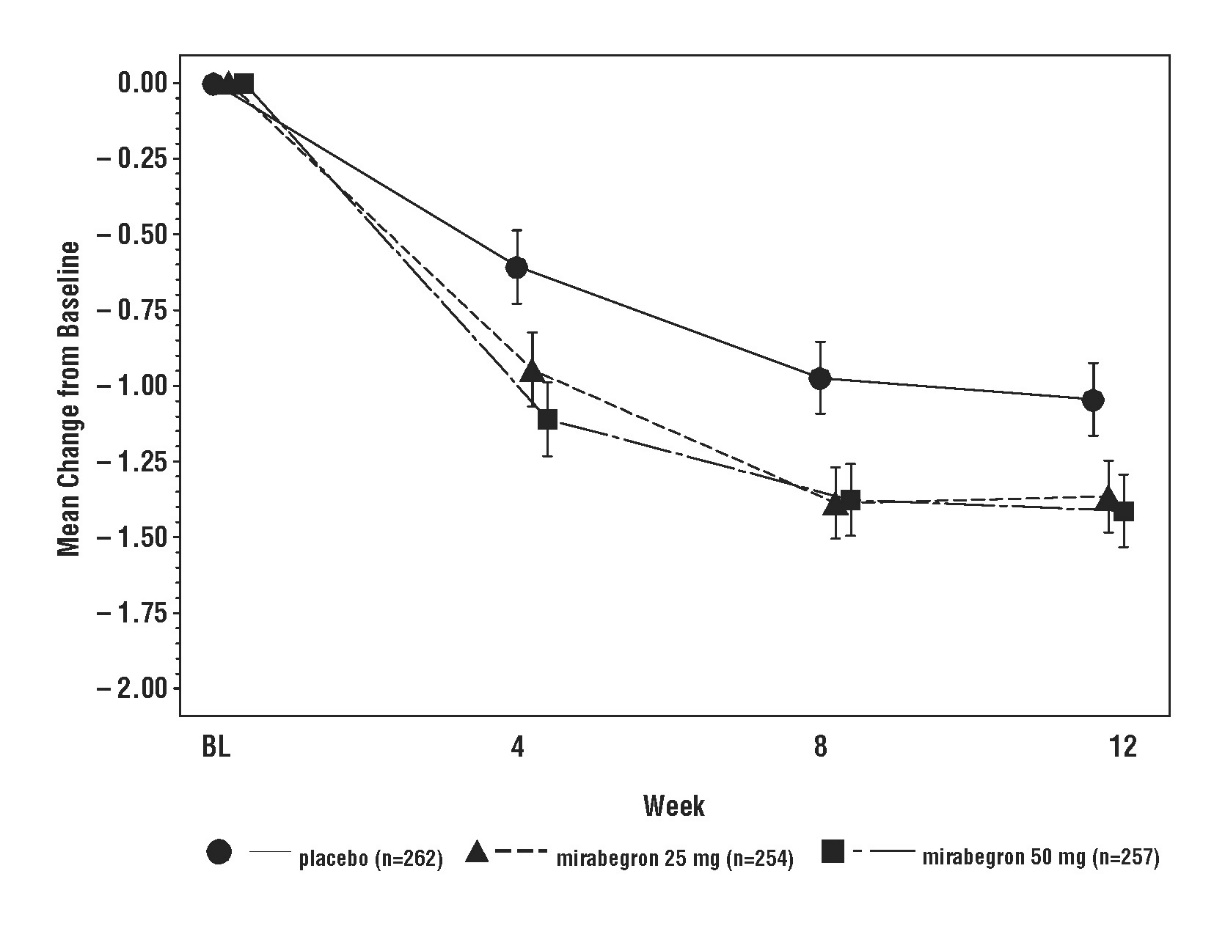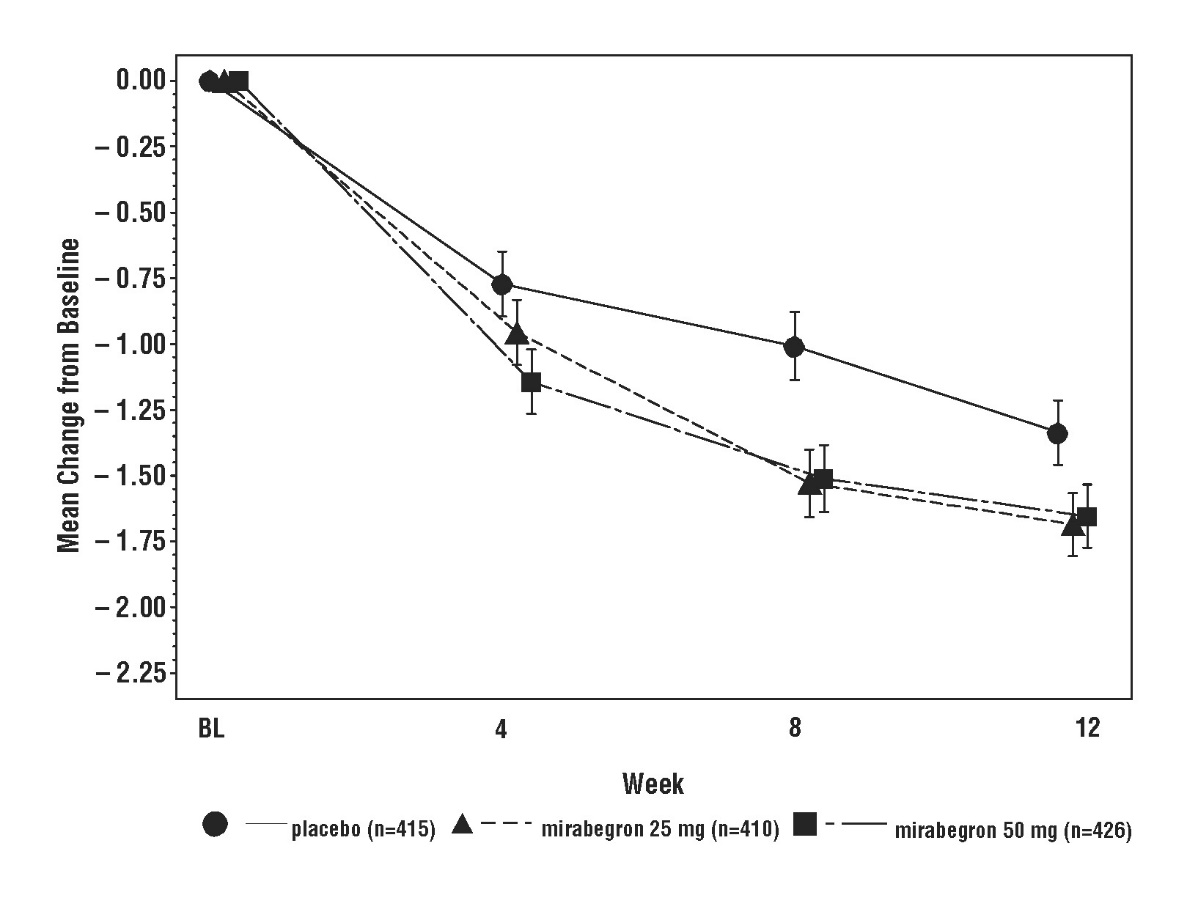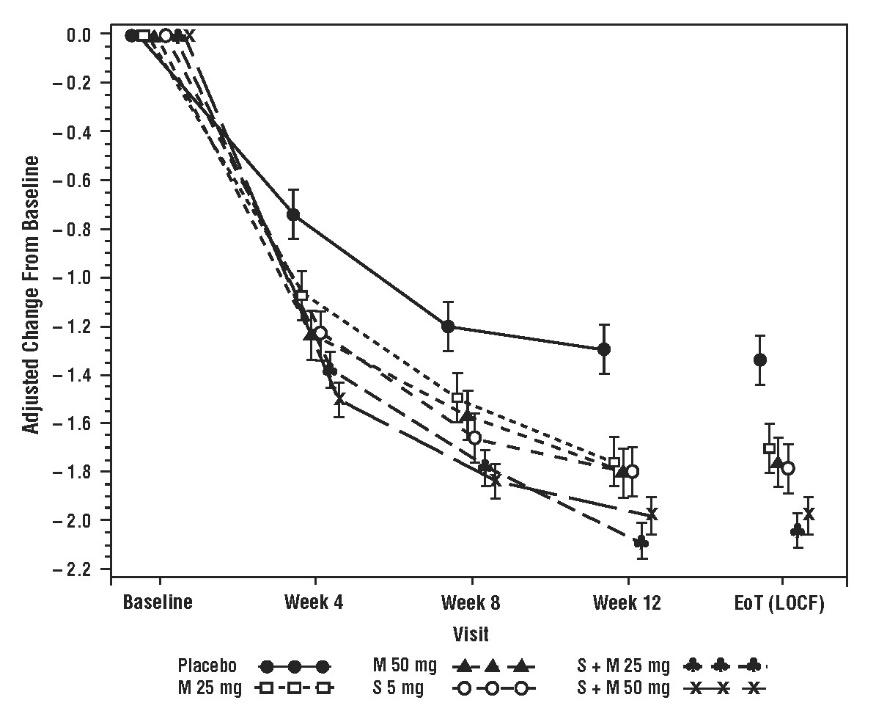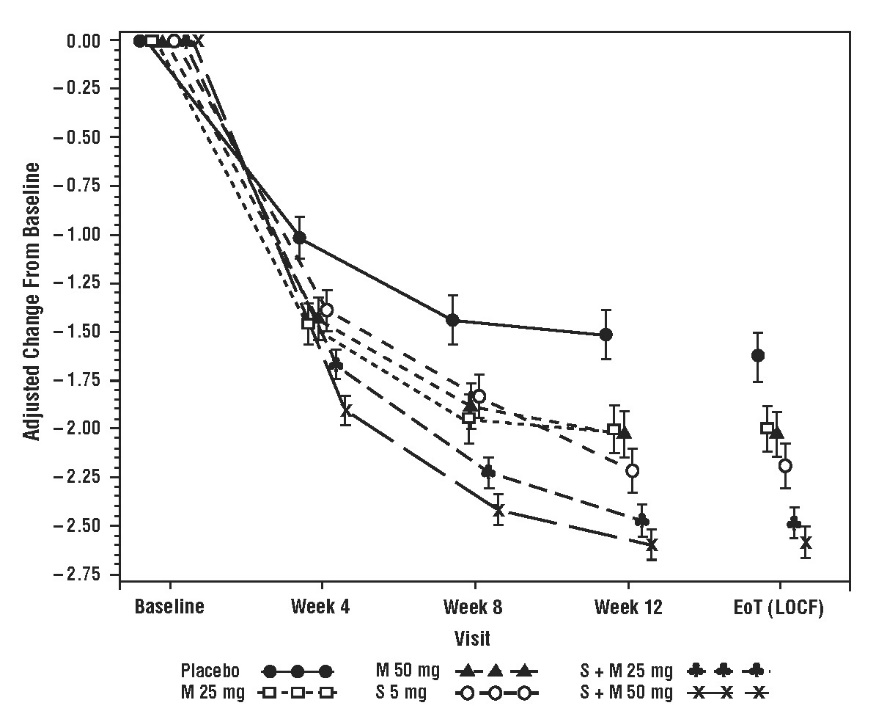 DRUG LABEL: Myrbetriq
NDC: 55154-8712 | Form: TABLET, FILM COATED, EXTENDED RELEASE
Manufacturer: Cardinal Health 107, LLC
Category: prescription | Type: HUMAN PRESCRIPTION DRUG LABEL
Date: 20251106

ACTIVE INGREDIENTS: MIRABEGRON 25 mg/1 1
INACTIVE INGREDIENTS: BUTYLATED HYDROXYTOLUENE; HYDROXYPROPYL CELLULOSE (1600000 WAMW); HYPROMELLOSE 2910 (6 MPA.S); MAGNESIUM STEARATE; POLYETHYLENE GLYCOL 8000; POLYETHYLENE OXIDE 2000000; FERRIC OXIDE RED; FERRIC OXIDE YELLOW

HIGHLIGHTS OF PRESCRIBING INFORMATION

These highlights do not include all the information needed to use MYRBETRIQ®/MYRBETRIQ® GRANULES safely and effectively. See full prescribing information for MYRBETRIQ/MYRBETRIQ GRANULES.
MYRBETRIQ (mirabegron extended-release tablets), for oral use
MYRBETRIQ GRANULES (mirabegron for extended-release oral suspension)
Initial U.S. Approval: 2012

RECENT MAJOR CHANGES

Indications and Usage (1.2) 3/2021
Dosage and Administration (2) 3/2021

Warnings and Precautions, Increase in Blood Pressure (5.1) 3/2021

1 INDICATIONS AND USAGE

MYRBETRIQ is a beta-3 adrenergic agonist indicated for the treatment of:

- Overactive bladder (OAB) in adult patients with symptoms of urge urinary incontinence, urgency, and urinary frequency, either alone or in combination with the muscarinic antagonist solifenacin succinate. (1.1)
- Neurogenic detrusor overactivity (NDO) in pediatric patients aged 3 years and older and weighing 35 kg or more. (1.2)

MYRBETRIQ Granules is a beta-3 adrenergic agonist indicated for the treatment of NDO in pediatric patients aged 3 years and older. (1.2)

2 DOSAGE AND ADMINISTRATION

- MYRBETRIQ and MYRBETRIQ Granules are two different products and they are not substitutable on a milligram-per-milligram basis. Select the recommended product (MYRBETRIQ or MYRBETRIQ Granules) based on the indication and patient’s weight. Do not combine MYRBETRIQ and MYRBETRIQ Granules to achieve the total dose. A recommended dosage for MYRBETRIQ Granules for adults has not been determined. (2.1)
  OAB in Adults
- The recommended starting dose of MYRBETRIQ is 25 mg orally once daily, either alone or in combination with solifenacin succinate 5 mg orally once daily. (2.2)
- After 4 to 8 weeks, the MYRBETRIQ dose may be increased to 50 mg orally once daily. (2.2)
  NDO in Pediatric Patients 3 Years and Older
- Pediatric Patients weighing less than 35 kg: Use MYRBETRIQ Granules: The recommended starting dose of MYRBETRIQ Granules is weight-based and administered as an extended-release oral suspension once daily. After 4 to 8 weeks, increase to the lowest effective dose without exceeding the maximum recommended dose. (2.3)
- Pediatric Patients weighing 35 kg or more: Use MYRBETRIQ or MYRBETRIQ Granules:
  - The recommended starting dosage of MYRBETRIQ is 25 mg orally once daily. After 4 to 8 weeks, the MYRBETRIQ dose may be increased to 50 mg orally once daily. (2.3)
  - The recommended starting dosage of MYRBETRIQ Granules, administered as an extended-release oral suspension, is 6 mL (48 mg) orally once daily. After 4 to 8 weeks, increase to a maximum dosage of MYRBETRIQ Granules 10 mL (80 mg) orally once daily (2.3)

Adult or Pediatric Patients with Renal or Hepatic Impairment: Refer to the full prescribing information for recommended dosage. (2.4, 2.5)

Preparation for MYRBETRIQ Granules: Refer to the full prescribing information. (2.6)
Administration

- MYRBETRIQ:
  - Adult patients: Swallow MYRBETRIQ whole with water. Do not chew, divide, or crush. Take with or without food. (2.7)
  - Pediatric patients: Swallow MYRBETRIQ whole with water. Do not chew, divide, or crush. Take with food. (2.7)
- MYRBETRIQ Granules:
  - Pediatric patients: Take MYRBETRIQ Granules prepared as an extended-release oral suspension. Take with food. (2.7)

3 DOSAGE FORMS AND STRENGTHS

- Extended-release tablets: 25 mg and 50 mg (3)
- For extended-release oral suspension: 8 mg/mL of mirabegron after reconstitution (3)

4 CONTRAINDICATIONS

Hypersensitivity to mirabegron or any inactive ingredients. (4)

5 WARNINGS AND PRECAUTIONS

- Increases in Blood Pressure: Can increase blood pressure in adult or pediatric patients. Periodically monitor blood pressure, especially in hypertensive patients. MYRBETRIQ/MYRBETRIQ Granules are not recommended in patients with severe uncontrolled hypertension. (5.1)
- Urinary Retention in Patients With Bladder Outlet Obstruction and in Patients Taking Muscarinic Antagonist Drugs for Overactive Bladder: Administer with caution in these patients because of risk of urinary retention. (5.2)
- Angioedema: Angioedema of the face, lips, tongue, and/or larynx has been reported with mirabegron. (5.3, 6.2)

6 ADVERSE REACTIONS

- Most commonly reported adverse reactions with MYRBETRIQ monotherapy in adult patients with OAB (> 2% and > placebo) were hypertension, nasopharyngitis, urinary tract infection, and headache. (6.1)
- Most commonly reported adverse reactions with MYRBETRIQ, in combination with solifenacin succinate in adult patients with OAB (> 2% and > placebo and > comparator), were dry mouth, urinary tract infection, constipation, and tachycardia. (6.1)
- Most commonly reported adverse reactions with MYRBETRIQ/MYRBETRIQ Granules in pediatric patients with NDO (≥ 3%) were UTI, nasopharyngitis, constipation, and headache. (6.1)

To report SUSPECTED ADVERSE REACTIONS, contact Astellas Pharma US, Inc. at 1-800-727-7003 or FDA at 1-800-FDA-1088 or www.fda.gov/medwatch.

7 DRUG INTERACTIONS

- Drugs Metabolized by CYP2D6: Mirabegron is a CYP2D6 inhibitor and, when used concomitantly with drugs metabolized by CYP2D6, especially narrow therapeutic index drugs, appropriate monitoring and possible dose adjustment of those drugs may be necessary. (5.4, 7.1, 12.3)
- Digoxin: When initiating a combination of mirabegron and digoxin with or without solifenacin succinate, use the lowest dose of digoxin; monitor serum digoxin concentrations to titrate digoxin dose to desired clinical effect. (7.2, 12.3)

FULL PRESCRIBING INFORMATION

1 INDICATIONS AND USAGE

1.1 Adult Overactive Bladder (OAB)

MYRBETRIQ Monotherapy

MYRBETRIQ® is indicated for the treatment of OAB in adult patients with symptoms of urge urinary incontinence, urgency, and urinary frequency.

MYRBETRIQ Combination Therapy with Solifenacin Succinate

MYRBETRIQ, in combination with the muscarinic antagonist solifenacin succinate, is indicated for the treatment of OAB in adult patients with symptoms of urge urinary incontinence, urgency, and urinary frequency.

1.2 Pediatric Neurogenic Detrusor Overactivity (NDO)

MYRBETRIQ Granules

MYRBETRIQ® Granules is indicated for the treatment of NDO in pediatric patients aged 3 years and older.

MYRBETRIQ

MYRBETRIQ is indicated for the treatment of NDO in pediatric patients aged 3 years and older and weighing 35 kg or more.

2 DOSAGE AND ADMINISTRATION

2.1 Important Dosage Information

MYRBETRIQ and MYRBETRIQ Granules are two different products and they are not substitutable on a milligram-per-milligram basis:

• Select the recommended product (MYRBETRIQ or MYRBETRIQ Granules) based on the indication and patient’s weight [see Indications and Usage (1) and Dosage and Administration (2.2, 2.3, 2.4, 2.5)].
• Do not combine MYRBETRIQ and MYRBETRIQ Granules to achieve the total dose.
• A recommended dosage for MYRBETRIQ Granules for adults has not been determined.

2.2 Recommended Dosage for Adult Patients with OAB

MYRBETRIQ Monotherapy

The recommended starting dosage of MYRBETRIQ is 25 mg orally once daily. If needed, increase to the maximum dosage of MYRBETRIQ 50 mg orally once daily after 4 to 8 weeks. For administration instructions, see Dosage and Administration (2.7).

MYRBETRIQ Combination Therapy with Solifenacin Succinate

The recommended starting dosage for combination treatment is MYRBETRIQ 25 mg orally once daily and solifenacin succinate 5 mg orally once daily. If needed, increase to the maximum dosage of MYRBETRIQ 50 mg orally once daily after 4 to 8 weeks. Refer to the Prescribing Information for solifenacin succinate for additional information. For administration instructions, see Dosage and Administration (2.7).

2.3 Recommended Dosage for Pediatric Patients Aged 3 Years and Older with NDO

For pediatric patients 3 years of age and older, select the appropriate product (MYRBETRIQ or MYRBETRIQ Granules) based on the patient’s weight.

Pediatric Patients weighing less than 35 kg: Use MYRBETRIQ Granules

The recommended starting and maximum doses of MYRBETRIQ Granules, administered as extended-release oral suspension once daily [see Dosage and Administration (2.6)], are shown in Table 1. The recommended dosages are determined based on patient weight. Evaluate patients periodically for potential dosage adjustment. For administration instructions, see Dosage and Administration (2.7).

Table 1: MYRBETRIQ Granules Recommended Dosage for Pediatric Patients Aged 3 Years and Older Weighing Less Than 35 kg as an Extended-Release Oral Suspension (Administered Orally Once Daily)
Body Weight Range | Starting Dose | Maximum Volume
11 kg to less than 22 kg | 3 mL (24 mg) | 6 mL (48 mg)
22 kg to less than 35 kg | 4 mL (32 mg) | 8 mL (64 mg)
Greater than or equal to 35 kg | Refer to information in next section

Pediatric Patients weighing 35 kg or more: Use MYRBETRIQ or MYRBETRIQ Granules

The recommended starting dosage of MYRBETRIQ is 25 mg orally once daily. If needed, increase to a maximum dosage of MYRBETRIQ 50 mg orally once daily after 4 to 8 weeks. For administration instructions, see Dosage and Administration (2.7).

The recommended starting dosage of MYRBETRIQ Granules is 6 mL (48 mg) orally once daily. If needed, increase to a maximum dosage of MYRBETRIQ Granules 10 mL (80 mg) orally once daily after 4 to 8 weeks. For administration instructions, see Dosage and Administration (2.7).

2.4 Recommended Dosage in Adult Patients with Renal or Hepatic Impairment

Dosage in Adults with Renal Impairment

The recommended dosage of MYRBETRIQ (administered orally once daily) in adult patients with renal impairment is described in Table 2 [see Use in Specific Populations (8.6)]. For administration instructions, see Dosage and Administration (2.7).

Table 2: MYRBETRIQ Recommended Dosage in Adult Patients with Renal Impairment (Administered Orally Once Daily)
Estimated GFR [Estimated GFR using the modification of diet in renal disease (MDRD) formula] | Starting Dose | Maximum Dose
eGFR 30 to 89 mL/min/1.73 m^2 | 25 mg | 50 mg
eGFR 15 to 29 mL/min/1.73 m^2 | 25 mg | 25 mg
eGFR < 15 mL/min/1.73 m^2 or requiring dialysis | Not recommended

Dosage in Adults with Hepatic Impairment

The recommended dosage of MYRBETRIQ (administered orally once daily) in adult patients with hepatic impairment is described in Table 3 [see Use in Specific Populations (8.7)]. For administration instructions, see Dosage and Administration (2.7).

Table 3: MYRBETRIQ Recommended Dosage in Adult Patients with Hepatic Impairment (Administered Orally Once Daily)
Hepatic Impairment Classification | Starting Dose | Maximum Dose
Child-Pugh Class A (Mild hepatic impairment) | 25 mg | 50 mg
Child-Pugh Class B (Moderate hepatic impairment) | 25 mg | 25 mg
Child-Pugh Class C (Severe hepatic impairment) | Not Recommended

2.5 Recommended Dosage in Pediatric Patients with Renal or Hepatic Impairment

For pediatric patients 3 years of age and older, select the appropriate product (MYRBETRIQ or MYRBETRIQ Granules) based on the patient’s weight.

Pediatric Patients Weighing Less Than 35 kg with Renal or Hepatic Impairment: Use MYRBETRIQ Granules

Dosage in Pediatric Patients with Renal Impairment

The recommended dosage of MYRBETRIQ Granules in pediatric patients with renal impairment (administered orally once daily) is described in Table 4 [see Use in Specific Populations (8.6)]. For administration instructions, see Dosage and Administration (2.7).

Table 4: MYRBETRIQ Granules Recommended Dosage in Pediatric Patients Aged 3 Years and Older Weighing Less Than 35 kg with Renal Impairment (Administered Orally Once Daily)
Estimated GFR [Estimate GFR using a validated eGFR estimating equation for the pediatric age range of the approved indication.] | Body Weight Range | Starting Dose | Maximum Dose
eGFR 30 to 89 mL/min/1.73 m^2 | 11 kg to less than 22 kg | 3 mL (24 mg) | 6 mL (48 mg)
eGFR 30 to 89 mL/min/1.73 m^2 | 22 kg to less than 35 kg | 4 mL (32 mg) | 8 mL (64 mg)
eGFR 15 to 29 mL/min/1.73 m^2 | 11 kg to less than 22 kg | 3 mL (24 mg) | 3 mL (24 mg)
eGFR 15 to 29 mL/min/1.73 m^2 | 22 kg to less than 35 kg | 4 mL (32 mg) | 4 mL (32 mg)
eGFR < 15 mL/min/1.73 m^2 or undergoing dialysis | Use is Not Recommended

Dosage in Pediatric Patients with Hepatic Impairment

The recommended dosage of MYRBETRIQ Granules in pediatric patients with hepatic impairment (administered orally once daily) is described in Table 5 [see Use in Specific Populations (8.7)]. For administration instructions, see Dosage and Administration (2.7).

Table 5: MYRBETRIQ Granules Recommended Dosage in Pediatric Patients Aged 3 Years and Older Weighing Less Than 35 kg with Hepatic Impairment (Administered Orally Once Daily)
Hepatic Impairment Classification | Body Weight Range | Starting Dose | Maximum Dose
Child-Pugh Class A (Mild hepatic impairment) | 11 kg to less than 22 kg | 3 mL (24 mg) | 6 mL (48 mg)
Child-Pugh Class A (Mild hepatic impairment) | 22 kg to less than 35 kg | 4 mL (32 mg) | 8 mL (64 mg)
Child-Pugh Class B (Moderate hepatic impairment) | 11 kg to less than 22 kg | 3 mL (24 mg) | 3 mL (24 mg)
Child-Pugh Class B (Moderate hepatic impairment) | 22 kg to less than 35 kg | 4 mL (32 mg) | 4 mL (32 mg)
Child-Pugh Class C (Severe hepatic impairment) | Use is Not Recommended

Pediatric Patients weighing 35 kg or more with renal or hepatic impairment: Use MYRBETRIQ or MYRBETRIQ Granules

Dosage in Pediatric Patients with Renal Impairment

The recommended dosage of MYRBETRIQ in pediatric patients with renal impairment weighing 35 kg or more (administered orally once daily) is described in Table 2 (above). Note that the dosage is the same as for adult patients with renal impairment [see Dosage and Administration (2.4) and Use in Specific Populations (8.6)]. For administration instructions, see Dosage and Administration (2.7).

The recommended dosage of MYRBETRIQ Granules in pediatric patients with renal impairment weighing 35 kg or more (administered orally once daily) is described in Table 6 [see Use in Specific Populations (8.6)]. For administration instructions, see Dosage and Administration (2.7).

Table 6: MYRBETRIQ Granules Recommended Dosage in Pediatric Patients Aged 3 Years and Older with Renal Impairment Weighing 35 kg or More (Administered Orally Once Daily)
Estimated GFR [Estimate GFR using a validated eGFR estimating equation for the pediatric age range of the approved indication.] | Starting Dose | Maximum Dose
eGFR 30 to 89 mL/min/1.73 m^2 | 6 mL (48 mg) | 10 mL (80 mg)
eGFR 15 to 29 mL/min/1.73 m^2 | 6 mL (48 mg) | 6 mL (48 mg)
eGFR < 15 mL/min/1.73 m^2 or undergoing dialysis | Use is Not Recommended

Dosage in Pediatric Patients with Hepatic Impairment

The recommended dosage of MYRBETRIQ in pediatric patients with hepatic impairment weighing 35 kg or more (administered orally once daily) is described in Table 3 (above). Note that the dosage is the same as for adult patients with hepatic impairment [see Dosage and Administration (2.4) and Use in Specific Populations (8.6)]. For administration instructions, see Dosage and Administration (2.7).

The recommended dosage of MYRBETRIQ Granules in pediatric patients with hepatic impairment weighing 35 kg or more (administered orally once daily) is described in Table 7 [see Use in Specific Populations (8.7)]. For administration instructions, see Dosage and Administration (2.7).

Table 7: MYRBETRIQ Granules Recommended Dosage in Pediatric Patients Aged 3 Years and Older with Hepatic Impairment Weighing 35 kg or More (Administered Orally Once Daily)
Hepatic Impairment Classification | Starting Dose | Maximum Dose
Child-Pugh Class A (Mild hepatic impairment) | 6 mL (48 mg) | 10 mL (80 mg)
Child-Pugh Class B (Moderate hepatic impairment) | 6 mL (48 mg) | 6 mL (48 mg)
Child-Pugh Class C (Severe hepatic impairment) | Use is Not Recommended

2.6 Preparation and Storage Instructions for MYRBETRIQ Granules

The required dose for MYRBETRIQ Granules (mirabegron for extended-release oral suspension) is calculated based on the weight of the patient. Prepare oral suspension at the time of dispensing.

Keep the bottle in the pouch up until the time of reconstitution.

• Discard the pouch and desiccant prior to reconstitution. Do not dispense.
• Tap the closed bottle several times to loosen the granules.
• Measure 100 mL of water, add the total amount to the bottle, and immediately shake vigorously for 1 minute, then let it stand for 10 to 30 minutes. Shake vigorously again for 1 minute.
• If granules have not dispersed, shake vigorously for another 1 minute.
• Record the 28-day expiration date on the container and carton based on the reconstitution date.
• Give the patient an appropriate dosing device.
• Store the reconstituted suspension at 20°C to 25°C (68°F to 77°F) for up to 28 days.
• Discard the unused portion after 28 days [see How Supplied/Storage and Handling (16.2)].

After reconstitution with 100 mL water, the suspension contains 8 mg/mL of mirabegron.

2.7 Administration Instructions

Administration instructions for MYRBETRIQ and MYRBETRIQ Granules differ based on the patient population.

MYRBETRIQ

Adult patients: Swallow MYRBETRIQ whole with water. Do not chew, divide, or crush. Take with or without food.

Pediatric patients: Swallow MYRBETRIQ whole with water. Do not chew, divide, or crush. Take with food [see Use in Specific Populations (8.4)].

MYRBETRIQ Granules

Adult patients: A recommended dosage for MYRBETRIQ Granules for adults has not been determined.

Pediatric patients: Take MYRBETRIQ Granules prepared as an extended-release oral suspension [see Dosage and Administration (2.6)]. Take with food to reduce potential exposure-related risks [see Use in Specific Populations (8.4)].

2.8 Missed Dose

Instruct patients to take any missed doses as soon as they remember, unless more than 12 hours have passed since the missed dose. If more than 12 hours have passed, the missed dose can be skipped, and the next dose should be taken at the usual time.

3 DOSAGE FORMS AND STRENGTHS

MYRBETRIQ (mirabegron extended-release tablets) are supplied in two different strengths as described below:

• 25 mg oval, brown, film-coated tablet, debossed with the (Astellas logo) and “325”

• 50 mg oval, yellow, film-coated tablet, debossed with the (Astellas logo) and “355”

MYRBETRIQ Granules (mirabegron for extended-release oral suspension): Each bottle is filled with approximately 8.3 g of yellowish white granules, which contain 830 mg of mirabegron. After reconstitution with 100 mL water, the oral suspension is pale brownish yellow to yellow with 8 mg/mL of mirabegron.

4 CONTRAINDICATIONS

MYRBETRIQ/MYRBETRIQ Granules is contraindicated in patients with known hypersensitivity reactions to mirabegron or any inactive ingredients of the tablet or oral suspension [see Adverse Reactions (6.1, 6.2)].

5 WARNINGS AND PRECAUTIONS

5.1 Increases in Blood Pressure

Increases in Blood Pressure in Adults

MYRBETRIQ/MYRBETRIQ Granules can increase blood pressure. Periodic blood pressure determinations are recommended, especially in hypertensive patients. MYRBETRIQ/MYRBETRIQ Granules is not recommended for use in patients with severe uncontrolled hypertension (defined as systolic blood pressure greater than or equal to 180 mm Hg and/or diastolic blood pressure greater than or equal to 110 mm Hg) [see Clinical Pharmacology (12.2)].

In two, randomized, placebo-controlled, healthy adult volunteer studies, MYRBETRIQ was associated with dose-related increases in supine blood pressure. In these studies, at the maximum recommended dose of 50 mg, the mean maximum increase in systolic/diastolic blood pressure was approximately 3.5/1.5 mm Hg greater than placebo.

In contrast, in adult OAB patients in clinical trials, MYRBETRIQ, taken as monotherapy or in combination with solifenacin succinate 5 mg, the mean increase in systolic and diastolic blood pressure at the maximum recommended mirabegron dose of 50 mg was approximately 0.5 to 1 mm Hg greater than placebo. Worsening of pre-existing hypertension was reported infrequently in patients taking MYRBETRIQ.

Increases in Blood Pressure in Pediatric Patients 3 Years and Older

MYRBETRIQ/MYRBETRIQ Granules can increase blood pressure in pediatric patients. Blood pressure increases may be larger in children (3 to less than 12 years of age) than in adolescents (12 to less than 18 years of age). Periodic blood pressure determinations are recommended. MYRBETRIQ/MYRBETRIQ Granules is not recommended for use in pediatric patients with severe uncontrolled hypertension, defined as a systolic and/or diastolic blood pressure above the 99th percentile plus 5 mm Hg for age, sex, and stature using appropriate reference values [see Adverse Reactions (6.1)].

5.2 Urinary Retention in Patients with Bladder Outlet Obstruction and in Patients Taking Muscarinic Antagonist Medications for OAB

In patients taking MYRBETRIQ, urinary retention has been reported to occur in patients with bladder outlet obstruction (BOO) and in patients taking muscarinic antagonist medications for the treatment of OAB. A controlled clinical safety study in patients with BOO did not demonstrate increased urinary retention in patients treated with mirabegron; however, MYRBETRIQ should still be administered with caution to patients with clinically significant BOO. For example, monitor these patients for signs and symptoms of urinary retention. MYRBETRIQ should also be administered with caution to patients taking muscarinic antagonist medications for the treatment of OAB, including solifenacin succinate [see Clinical Pharmacology (12.2)].

5.3 Angioedema

Angioedema of the face, lips, tongue, and/or larynx has been reported with MYRBETRIQ/MYRBETRIQ Granules. In some cases, angioedema occurred after the first dose, however, cases have been reported to occur hours after the first dose or after multiple doses. Angioedema, associated with upper airway swelling, may be life-threatening. If involvement of the tongue, hypopharynx, or larynx occurs, promptly discontinue MYRBETRIQ/MYRBETRIQ Granules and provide appropriate therapy and/or measures necessary to ensure a patent airway [see Adverse Reactions (6.2)].

5.4 Patients Taking Drugs Metabolized by CYP2D6

Since MYRBETRIQ/MYRBETRIQ Granules is a moderate CYP2D6 inhibitor, the systemic exposure to CYP2D6 substrates is increased when coadministered with MYRBETRIQ/MYRBETRIQ Granules. Therefore, appropriate monitoring and dose adjustment may be necessary, especially with narrow therapeutic index drugs metabolized by CYP2D6 [see Drug Interactions (7.1) and Clinical Pharmacology (12.3)].

6 ADVERSE REACTIONS

The following adverse reactions are discussed in more detail in other sections of the labeling.

- Hypertension [see Warnings and Precautions (5.1)]
- Urinary Retention [see Warnings and Precautions (5.2)]
- Angioedema [see Warnings and Precautions (5.3)]

6.1 Clinical Trials Experience

Because clinical trials are conducted under widely varying conditions, adverse reaction rates observed in the clinical trials of a drug cannot be directly compared to rates in the clinical trials of another drug and may not reflect the rates observed in clinical practice.

MYRBETRIQ Monotherapy for Adult OAB

In three, 12-week, double-blind, placebo-controlled, safety and efficacy studies in patients with OAB (Studies 1, 2, and 3), MYRBETRIQ was evaluated for safety in 2736 patients [see Clinical Studies (14.1)]. Study 1 also included an active control. For the combined Studies 1, 2, and 3, 432 patients received MYRBETRIQ 25 mg, 1375 received MYRBETRIQ 50 mg, and 929 received MYRBETRIQ 100 mg once daily. In these studies, the majority of the patients were Caucasian (94%) and female (72%) with a mean age of 59 years (range 18 to 95 years).

MYRBETRIQ was also evaluated for safety in 1632 patients who received MYRBETRIQ 50 mg once daily (n=812 patients) or MYRBETRIQ 100 mg (n=820 patients) in a 1-year, randomized, fixed-dose, double-blind, active-controlled, safety study in patients with OAB (Study 4). Of these patients, 731 received MYRBETRIQ in a previous 12-week study. In Study 4, 1385 patients received MYRBETRIQ continuously for at least 6 months, 1311 patients received MYRBETRIQ for at least 9 months, and 564 patients received MYRBETRIQ for at least 1 year.

The most frequent adverse events (0.2%) leading to discontinuation in Studies 1, 2, and 3 for the 25 mg or 50 mg dose were nausea, headache, hypertension, diarrhea, constipation, dizziness, and tachycardia.

Atrial fibrillation (0.2%) and prostate cancer (0.1%) were reported as serious adverse events by more than 1 patient and at a rate greater than placebo.

Table 8 lists the adverse reactions, derived from all adverse events, that were reported in Studies 1, 2, and 3 at an incidence greater than placebo and in 1% or more of patients treated with MYRBETRIQ 25 mg or 50 mg once daily for up to 12 weeks. The most commonly reported adverse reactions (greater than 2% of MYRBETRIQ patients and greater than placebo) were hypertension, nasopharyngitis, urinary tract infection, and headache.

Table 8: Percentages of Patients with Adverse Reactions, Derived from All Adverse Events, Exceeding Placebo Rate and Reported in ≥ 1% of OAB Patients Treated with MYRBETRIQ 25 mg or 50 mg Once Daily in Studies 1, 2, and 3
Adverse Reaction | Placebo; (%) | MYRBETRIQ 25 mg; (%) | MYRBETRIQ 50 mg; (%)
Number of Patients | 1380 | 432 | 1375
Hypertension [Includes reports of blood pressure above the normal range, and BP increased from baseline, occurring predominantly in subjects with baseline hypertension.] | 7.6 | 11.3 | 7.5
Nasopharyngitis | 2.5 | 3.5 | 3.9
Urinary Tract Infection | 1.8 | 4.2 | 2.9
Headache | 3.0 | 2.1 | 3.2
Constipation | 1.4 | 1.6 | 1.6
Upper Respiratory Tract Infection | 1.7 | 2.1 | 1.5
Arthralgia | 1.1 | 1.6 | 1.3
Diarrhea | 1.3 | 1.2 | 1.5
Tachycardia | 0.6 | 1.6 | 1.2
Abdominal Pain | 0.7 | 1.4 | 0.6
Fatigue | 1.0 | 1.4 | 1.2

Other adverse reactions reported by less than 1% of patients treated with MYRBETRIQ in Studies 1, 2, or 3 included:

Cardiac disorders: palpitations, blood pressure increased [see Clinical Pharmacology (12.2)]
Eye disorders: glaucoma [see Clinical Pharmacology (12.2)]
Gastrointestinal disorders: dyspepsia, gastritis, abdominal distension
Infections and Infestations: sinusitis, rhinitis
Investigations: GGT increased, AST increased, ALT increased, LDH increased
Renal and urinary disorders: nephrolithiasis, bladder pain
Reproductive system and breast disorders: vulvovaginal pruritus, vaginal infection
Skin and subcutaneous tissue disorders: urticaria, leukocytoclastic vasculitis, rash, pruritus, purpura, lip edema

Table 9 lists the rates of the most commonly reported adverse reactions, derived from all adverse events in patients treated with MYRBETRIQ 50 mg for up to 52 weeks in Study 4. The most commonly reported adverse reactions (> 3% of MYRBETRIQ patients) were hypertension, urinary tract infection, headache, and nasopharyngitis.

Table 9: Percentages of Patients with Adverse Reactions, Derived from All Adverse Events, Reported in > 2% of OAB Patients Treated with MYRBETRIQ 50 mg Once Daily in Study 4
Adverse Reaction | MYRBETRIQ 50 mg; (%) | Active Control; (%)
Number of Patients | 812 | 812
Hypertension | 9.2 | 9.6
Urinary Tract Infection | 5.9 | 6.4
Headache | 4.1 | 2.5
Nasopharyngitis | 3.9 | 3.1
Back Pain | 2.8 | 1.6
Constipation | 2.8 | 2.7
Dry Mouth | 2.8 | 8.6
Dizziness | 2.7 | 2.6
Sinusitis | 2.7 | 1.5
Influenza | 2.6 | 3.4
Arthralgia | 2.1 | 2.0
Cystitis | 2.1 | 2.3

In Study 4, in patients treated with MYRBETRIQ 50 mg once daily, adverse reactions leading to discontinuation reported by more than 2 patients and at a rate greater than active control included: constipation (0.9%), headache (0.6%), dizziness (0.5%), hypertension (0.5%), dry eyes (0.4%), nausea (0.4%), vision blurred (0.4%), and urinary tract infection (0.4%). Serious adverse events reported by at least 2 patients and exceeding active control included cerebrovascular accident (0.4%) and osteoarthritis (0.2%). Serum ALT/AST increased from baseline by greater than 10-fold in 2 patients (0.3%) taking MYRBETRIQ 50 mg; and these markers subsequently returned to baseline while both patients continued MYRBETRIQ.

In Study 4, serious adverse events of neoplasm were reported by 0.1%, 1.3%, and 0.5% of patients treated with MYRBETRIQ 50 mg, MYRBETRIQ 100 mg, and active control once daily, respectively. Neoplasms reported by 2 patients treated with MYRBETRIQ 100 mg included breast cancer, lung neoplasm malignant, and prostate cancer. A causal relationship between mirabegron and these reported neoplasms has not been established.

In a separate clinical study in Japan, a single case was reported as Stevens-Johnson syndrome with increased serum ALT, AST, and bilirubin in a patient taking MYRBETRIQ 100 mg as well as an herbal medication (Kyufu Gold).

MYRBETRIQ Combination Therapy with Solifenacin Succinate for Adult OAB

In three, 12-week, double-blind, randomized, active-controlled safety and efficacy studies in patients with OAB (Studies 5, 6, and 7), combination treatment of MYRBETRIQ and solifenacin succinate was evaluated for safety in 6818 patients [see Clinical Studies (14.2)]. Studies 5 and 6 also included a placebo control. For the combined Studies 5, 6, and 7, 997 patients received combination treatment with MYRBETRIQ 25 mg and solifenacin succinate 5 mg, and 1706 patients received combination treatment with MYRBETRIQ 50 mg and solifenacin succinate 5 mg. In these studies, the majority of the patients were Caucasian (88%) and female (77%) with a mean age of 57 years (range 18 to 89 years).

MYRBETRIQ 50 mg and solifenacin succinate 5 mg coadministration was also evaluated for safety in 1814 patients in a 52-week, double-blind, randomized, active-controlled study in patients with OAB (Study 8) [see Clinical Studies (14.2)].

In Studies 5, 6, and 7, the most commonly reported adverse reactions (greater than 2% of patients treated with combination therapy of MYRBETRIQ and solifenacin succinate 5 mg, and greater than placebo and/or MYRBETRIQ or solifenacin succinate comparator at the same dose as in the combination treatment) were dry mouth, urinary tract infection, constipation, and tachycardia. The most frequent adverse reactions (≥ 0.2%) leading to discontinuation in the coadministration trials were dry mouth and urinary retention.

Table 10 lists the adverse reactions, derived from all adverse events that were reported in Studies 5, 6, and 7 in 1% or more of patients treated with MYRBETRIQ 25 mg or 50 mg coadministered with solifenacin succinate 5 mg and at an incidence greater than placebo and mirabegron or solifenacin succinate comparator at the same dose as in the combination treatment when administered once daily for up to 12 weeks.

Table 10: Percentages of Patients with Adverse Reactions, Derived from All Adverse Events, Exceeding Placebo and Comparator (at same dose level) Rate and Reported in ≥ 1% of OAB Patients Treated with Combination Therapy in Studies 5, 6, and 7 [Adverse reactions occurring in patients treated with coadministration of MYRBETRIQ and solifenacin succinate in Study 7, that included a 4-week initial treatment period with MYRBETRIQ 25 mg + Solifenacin Succinate 5 mg, are included in the MYRBETRIQ 50 mg + Solifenacin Succinate 5 mg group.]
Adverse; Reaction | Placebo; (%) | MYRBETRIQ; 25 mg; (%) | MYRBETRIQ; 50 mg; (%) | Solifenacin Succinate; 5 mg; (%) | MYRBETRIQ; 25 mg + Solifenacin Succinate; 5 mg; (%) | MYRBETRIQ; 50 mg + Solifenacin Succinate; 5 mg; (%)
Number of Patients | 510 | 500 | 500 | 1288 | 997 | 1706
Dry Mouth | 2.2 | 3.8 | 3.6 | 6.5 | 9.3 | 7.2
Urinary Tract Infections [Includes any recorded treatment-emergent UTI.] | 5.3 | 4.0 | 4.2 | 3.6 | 7.0 | 4.0
Constipation | 1.2 | 1.2 | 2.8 | 2.4 | 4.2 | 3.9
Tachycardia | 0.8 | 1.6 | 1.6 | 0.7 | 2.2 | 0.9
Dyspepsia | 0.6 | 0.4 | 0.2 | 0.7 | 1.1 | 1.3
Dizziness | 0.4 | 0.8 | 1.2 | 1.2 | 1.3 | 0.4
Vision Blurred | 0.4 | 0.2 | 0.2 | 0.9 | 0.7 | 1.1
Arthralgia | 0.8 | 0.8 | 0.8 | 0.8 | 0.5 | 1.1

In Study 8, the most common adverse reactions (more than 2% of patients treated with coadministration of MYRBETRIQ and solifenacin succinate and exceeding comparator rate) were UTI, dry mouth, constipation, and headache. The most frequent adverse reactions leading to discontinuation in the trial were constipation (0.2%), urinary retention (0.2%), urinary hesitation (0.2%), and vision blurred (0.2%).

In Study 8, serious adverse events of neoplasm were reported by 0.7%, 0.3%, and 0% of patients who received coadministration of MYRBETRIQ 50 mg and solifenacin succinate 5 mg, MYRBETRIQ 50 mg monotherapy, and solifenacin succinate 5 mg monotherapy, respectively. Neoplasms reported by more than 1 patient who received coadministration with MYRBETRIQ 50 mg and solifenacin succinate 5 mg included basal cell carcinoma (n=3), breast cancer (n=2), melanoma (n=2), and squamous cell carcinoma (n=2). A causal relationship between the coadministration of mirabegron and solifenacin succinate and these reported neoplasms has not been established.

Table 11 lists the adverse reactions, derived from all adverse events that were reported at an incidence greater than comparator and in 2% or more of patients treated with MYRBETRIQ 50 mg coadministered with solifenacin succinate 5 mg once daily for up to 52 weeks in Study 8.

Table 11: Percentages of Patients with Adverse Reactions, Derived from All Adverse Events, Exceeding Comparator Rate and Reported in ≥ 2% of OAB Patients Treated with Combination Therapy in Study 8
Adverse Reaction | MYRBETRIQ; 50 mg; (%) | Solifenacin Succinate; 5 mg; (%) | MYRBETRIQ; 50 mg + Solifenacin Succinate; 5 mg; (%)
Number of Patients | 305 | 303 | 1206
Urinary Tract Infections [Includes any recorded treatment-emergent UTI.] | 6.2 | 5.9 | 8.4
Dry Mouth | 3.9 | 5.9 | 6.1
Constipation | 1.0 | 2.3 | 3.3
Headache | 1.6 | 1.7 | 2.9

MYRBETRIQ/MYRBETRIQ Granules for Pediatric Neurogenic Detrusor Overactivity (NDO)

The safety of MYRBETRIQ/MYRBETRIQ Granules was evaluated in a 52-week, open-label, baseline-controlled, multicenter, dose titration study (Study 9) [see Clinical Studies (14.3)]. The study included 86 pediatric patients 3 to 17 years of age with neurogenic detrusor overactivity (NDO); 55% were female, 72% were White. Treatment was initiated at the weight-based starting recommended dose and was increased to a dose equivalent of MYRBETRIQ 50 mg daily dose in adults by Week 8. Subsequent to the dose titration period, patients continued their optimized dose for the duration of the 52-week study (mean exposure duration 303 days, range 1 to 390 days).

The most commonly reported adverse reactions were UTI, nasopharyngitis, constipation, and headache.

Table 12 lists the adverse reactions that were reported in 2% or more of patients treated with MYRBETRIQ/MYRBETRIQ Granules for oral suspension in Study 9.

Table 12: Percentages of Patients with Adverse Reactions Reported in ≥ 2% of Patients 3 to 17 Years of Age with Neurogenic Detrusor Overactivity (NDO) Treated with MYRBETRIQ/MYRBETRIQ Granules in Study 9
Adverse Reaction | Percentage (%) of Patients Reporting; Adverse Reactions; N=86
Number of Patients | 51 (59.3)
Urinary Tract Infection [Includes any recorded UTI while patient was on treatment with MYRBETRIQ/MYRBETRIQ Granules.] | 24.4
Nasopharyngitis | 5.8
Constipation | 4.7
Headache | 3.5
Nausea | 2.3
Gastroenteritis | 2.3
Rhinitis | 2.3
Cough | 2.3

Increased Blood Pressure in Pediatric Patients with NDO Treated with MYRBETRIQ/MYRBETRIQ Granules:

Mean systolic and diastolic blood pressures increased in Study 9 by 4.3 mm Hg and 1.7 mm Hg, respectively, in patients less than 12 years of age on MYRBETRIQ/MYRBETRIQ Granules at a dose equivalent of MYRBETRIQ 50 mg daily dose in adults. The blood pressure increases were larger in patients less than 8 years of age with mean systolic and diastolic blood pressure increases of 5.9 mm Hg and 2.3 mm Hg, respectively. Ten (24%) patients less than 12 years of age who were normotensive at baseline had at least one blood pressure measured at or above the 95th percentile for age, sex, and stature during Study 9. Stage 1 hypertension, defined as repeated blood pressure measurements at or above the 95th percentile for age, sex, and stature, was sustained in six of these 10 patients (60%) at the end of the study.

6.2 Postmarketing Experience

The following adverse reactions have been identified during post-approval use of MYRBETRIQ/MYRBETRIQ Granules. Because these reactions are reported voluntarily from a population of uncertain size, it is not always possible to reliably estimate their frequency or establish a causal relationship to drug exposure. The following events have been reported in association with mirabegron use in worldwide postmarketing experience:

Cardiac disorders: atrial fibrillation
Gastrointestinal disorders: nausea, constipation, diarrhea
Nervous system disorders: dizziness, headache

There have been postmarketing reports of confusion, hallucinations, insomnia, and anxiety in patients taking mirabegron. The majority of these patients had pre-existing medical conditions or concomitant medications that may cause confusion, hallucinations, insomnia, and anxiety. A causal relationship between mirabegron and these disorders has not been established.

Skin and subcutaneous tissue disorders: angioedema of the face, lips, tongue, and larynx, with or without respiratory symptoms [see Warnings and Precautions (5.3)]; pruritus
Renal and urinary disorders: urinary retention [see Warnings and Precautions (5.2)]

7 DRUG INTERACTIONS

Drug interaction studies were conducted in adult patients to investigate the effect of coadministered drugs on the pharmacokinetics of mirabegron and the effect of mirabegron on the pharmacokinetics of coadministered drugs (e.g., ketoconazole, rifampin, solifenacin succinate, tamsulosin, and oral contraceptives) [see Clinical Pharmacology (12.3)]. No dose adjustment is recommended when these drugs are coadministered with mirabegron.

The following are drug interactions for which monitoring is recommended:

7.1 Drugs Metabolized by CYP2D6

Since mirabegron is a moderate CYP2D6 inhibitor, the systemic exposure of drugs metabolized by CYP2D6 enzyme is increased when coadministered with mirabegron. Therefore, appropriate monitoring and dose adjustment may be necessary when MYRBETRIQ/MYRBETRIQ Granules is coadministered with these drugs, especially with narrow therapeutic index CYP2D6 substrates [see Warnings and Precautions (5.4) and Clinical Pharmacology (12.3)].

7.2 Digoxin

When given in combination, 100 mg mirabegron increased mean digoxin Cmax from 1.01 to 1.3 ng/mL (29%) and AUC from 16.7 to 19.3 ng.h/mL (27%). Concomitant administration of 0.25 mg digoxin with a combination of 5 mg solifenacin and 50 mg mirabegron increased digoxin AUCtau and Cmax by approximately 10% and 14%, respectively. For patients who are initiating a combination of mirabegron and digoxin, the lowest dose for digoxin should initially be considered. Serum digoxin concentrations should be monitored and used for titration of the digoxin dose to obtain the desired clinical effect [see Clinical Pharmacology (12.3)].

7.3 Warfarin

The mean Cmax of S- and R-warfarin was increased by approximately 4% and AUC by approximately 9% when administered as a single dose of 25 mg after multiple doses of 100 mg mirabegron. Following a single dose administration of 25 mg warfarin, mirabegron had no effect on the warfarin pharmacodynamic endpoints such as International Normalized Ratio (INR) and prothrombin time. However, the effect of mirabegron on multiple doses of warfarin and on warfarin pharmacodynamic end points such as INR and prothrombin time has not been fully investigated [see Clinical Pharmacology (12.3)].

8 USE IN SPECIFIC POPULATIONS

8.1 Pregnancy

Risk Summary

There are no studies with the use of MYRBETRIQ/MYRBETRIQ Granules in pregnant women or adolescents to inform a drug-associated risk of major birth defects, miscarriages, or adverse maternal or fetal outcomes. Mirabegron administration to pregnant animals during organogenesis resulted in reversible skeletal variations (in rats) at 22-fold (via AUC) the maximum recommended human dose (MRHD) of 50 mg/day and decreased fetal body weights (in rabbits) at 14-fold the MRHD. At maternally-toxic exposures in rats (96-fold), decreased fetal weight and increased fetal mortality were observed and, in rabbits (36-fold), cardiac findings (fetal cardiomegaly and fetal dilated aortae) were observed [see Data].

The estimated background risks of major birth defects and miscarriage for the indicated populations are unknown. In the U.S. general population, the estimated background risk of major birth defects or miscarriage in clinically recognized pregnancies are 2-4% and 15-20%, respectively.

Data

Animal Data

No embryo-fetal lethality or morphological fetal developmental abnormalities were produced in pregnant rats following daily oral administration of mirabegron during the period of organogenesis (Days 7 to 17 of gestation) at 0, 10, 30, 100, or 300 mg/kg, doses which were associated with systemic exposures (AUC) 0, 1, 6, 22, and 96-fold the MRHD. Skeletal variations (wavy ribs, delayed ossification) were observed in fetuses at doses 22-fold the systemic exposure at the MRHD and were reversible during development. Exposures 96-fold the MRHD were maternally-toxic (mortality, decreased body weight gain) and associated with fetal growth reduction.

Pregnant rabbits were treated with daily oral doses of mirabegron at 0, 3, 10, or 30 mg/kg/day during the period of organogenesis (Days 6 to 20 of gestation), which resulted in plasma exposures that were 0, 1, 14, or 36-fold the MRHD based on AUC. At 10 mg/kg/day (14-fold the MRHD) and higher, fetal body weights were reduced. At 30 mg/kg/day, maternal toxicity (increased heart rate, mortality, reduced body weight gain, reduced food consumption) occurred, and fetal deaths, fetal cardiomegaly and fetal dilated aortae were observed at systemic exposure levels (AUC) 36-fold the MRHD.

In a pre- and postnatal developmental study, rats were treated with daily oral doses of mirabegron at 0, 10, 30, or 100 mg/kg/day (0, 1, 6, or 22-fold the MRHD) from day 7 of gestation until day 20 after birth. Decreased maternal body weight was observed along with decreased pup survival in the first few days after birth (92.7% survival) compared to the control group (98.8% survival), at 100 mg/kg/day (22-fold the MRHD). Pup body weight gain was reduced until postnatal day 7 but not further affected throughout the remainder of the lactation period. In utero and lactational exposure did not affect developmental milestones, behavior, or fertility of offspring. No effects were observed at 30 mg/kg/day.

8.2 Lactation

Risk Summary

There are no data on the presence of mirabegron in human milk, the effects on the breastfed child, or the effects on milk production. Mirabegron-related material was present in rat milk and in the stomach of nursing pups following administrations of a single 10 mg/kg oral dose of ^14C-labeled mirabegron to lactating rats. When a drug is present in animal milk, it is likely that the drug will be present in human milk.

The developmental and health benefits of breastfeeding should be considered along with the mother’s clinical need for MYRBETRIQ/MYRBETRIQ Granules and any potential adverse effects on the breastfed child from mirabegron or from the underlying maternal condition.

8.4 Pediatric Use

The safety and effectiveness have been established only for the following pediatric indications:

- MYRBETRIQ: Treatment of neurogenic detrusor overactivity (NDO) in pediatric patients 3 years of age and older and weighing 35 kg or more.
- MYRBETRIQ Granules: Treatment of neurogenic detrusor overactivity (NDO) in pediatric patients 3 years of age and older.

The safety and effectiveness of MYRBETRIQ/MYRBETRIQ Granules in pediatric patients aged 3 years and older have been established for the treatment of neurogenic detrusor overactivity (NDO) and the information on this use is discussed throughout the labeling. Use of MYRBETRIQ/MYRBETRIQ Granules for this indication is supported by evidence from a 52-week, open-label, baseline-controlled, multicenter, dose titration trial in pediatric patients 3 years of age and older with NDO (Study 9) [see Adverse Reactions (6.1), Clinical Studies (14.3)]. Results showed an improvement from baseline in maximum cystometric (bladder) capacity (MCC) with MYRBETRIQ/MYRBETRIQ Granules use [see Clinical Studies (14.3)]. The most commonly reported adverse reactions in Study 9 (≥ 3%) were UTI, nasopharyngitis, constipation, and headache. Increased mean systolic and diastolic blood pressures with use of MYRBETRIQ/MYRBETRIQ Granules occurred in patients less than 12 years of age with larger increases in patients younger than 8 years of age [see Adverse Reactions (6.1)].
Take MYRBETRIQ/MYRBETRIQ Granules with food to reduce potential exposure-related risks, such as increased heart rate, as predicted by modeling of vital signs data in Study 9 [see Clinical Pharmacology (12.3)].

8.5 Geriatric Use

Of 5648 patients who received MYRBETRIQ monotherapy in the phase 2 and 3 studies for OAB, 2029 (35.9%) were 65 years of age or older, and 557 (9.9%) were 75 years of age or older. No overall differences in safety or effectiveness were observed between patients younger than 65 years of age and those 65 years of age or older in these studies.

8.6 Renal Impairment

MYRBETRIQ/MYRBETRIQ Granules have not been studied in patients with End-Stage Renal Disease (eGFR < 15 mL/min/1.73 m^2) or patients requiring hemodialysis and, therefore, is not recommended for use in these patient populations. No dose adjustment is necessary in patients with mild or moderate renal impairment (eGFR 30 to 89 mL/min/1.73 m^2).

In adult patients with severe renal impairment (eGFR 15 to 29 mL/min/1.73 m^2), the daily dose of MYRBETRIQ should not exceed 25 mg. In pediatric patients with severe renal impairment, the daily dose of MYRBETRIQ/MYRBETRIQ Granules should not exceed the recommended starting dose [see Clinical Pharmacology (12.3)].

8.7 Hepatic Impairment

MYRBETRIQ/MYRBETRIQ Granules have not been studied in patients with severe hepatic impairment (Child-Pugh Class C) and, therefore, is not recommended for use in this patient population. No dose adjustment is necessary in patients with mild hepatic impairment (Child-Pugh Class A).

In adult patients with moderate hepatic impairment (Child-Pugh Class B), the daily dose of MYRBETRIQ should not exceed 25 mg. In pediatric patients with moderate hepatic impairment (Child-Pugh Class B), the daily dose of MYRBETRIQ/MYRBETRIQ Granules should not exceed the recommended starting dose [see Clinical Pharmacology (12.3)].

10 OVERDOSAGE

Mirabegron has been administered to healthy volunteers at single doses up to 400 mg. At this dose, adverse events reported included palpitations (1 of 6 subjects) and increased pulse rate exceeding 100 beats per minute (bpm) (3 of 6 subjects). Multiple doses of mirabegron up to 300 mg daily for 10 days showed increases in pulse rate and systolic blood pressure when administered to healthy volunteers. Treatment for overdosage should be symptomatic and supportive. In the event of overdosage, pulse rate, blood pressure and ECG monitoring is recommended.

11 DESCRIPTION

MYRBETRIQ (mirabegron extended-release tablets) for oral use and MYRBETRIQ Granules (mirabegron for extended-release oral suspension) are beta-3 adrenergic agonists.

The chemical name of mirabegron is 2-(2-aminothiazol-4-yl)-N-[4-(2-{[(2R)-2-hydroxy-2-phenylethyl]amino}ethyl)phenyl]acetamide having an empirical formula of C21H24N4O2S and a molecular weight of 396.51. The structural formula of mirabegron is:

Mirabegron is a white powder. It is practically insoluble in water (0.082 mg/mL). It is soluble in methanol and dimethyl sulfoxide.

Each MYRBETRIQ (mirabegron extended-release tablets) for oral use contains either 25 mg or 50 mg of mirabegron and the following inactive ingredients: butylated hydroxytoluene, hydroxypropyl cellulose, hypromellose, magnesium stearate, polyethylene glycol, polyethylene oxide, red ferric oxide (25 mg tablet only), and yellow ferric oxide.

Each bottle of MYRBETRIQ Granules (mirabegron for extended-release oral suspension) contains approximately 8.3 g of granules, which contain 830 mg of mirabegron, and the following inactive ingredients: acesulfame potassium, diluted hydrochloric acid, ethylparaben, hypromellose, magnesium stearate, mannitol, methylparaben, silicon dioxide, simethicone, sodium polystyrene sulfonate, and xanthan gum. After reconstituted with 100 mL water, the suspension contains 8 mg/mL of mirabegron.

12 CLINICAL PHARMACOLOGY

12.1 Mechanism of Action

Mirabegron is an agonist of the human beta-3 adrenergic receptor (AR) as demonstrated by in vitro laboratory experiments using the cloned human beta-3 AR. Mirabegron relaxes the detrusor smooth muscle during the storage phase of the urinary bladder fill-void cycle by activation of beta-3 AR which increases bladder capacity. Although mirabegron showed very low intrinsic activity for cloned human beta-1 AR and beta-2 AR, results in humans indicate that beta-1 AR stimulation occurred at a mirabegron dose of 200 mg.

12.2 Pharmacodynamics

Urodynamics

The effects of mirabegron on maximum urinary flow rate and detrusor pressure at maximum flow rate were assessed in a urodynamic study consisting of 200 male patients with lower urinary tract symptoms (LUTS) and BOO. Administration of mirabegron once daily for 12 weeks did not adversely affect the mean maximum flow rate or mean detrusor pressure at maximum flow rate in this study. Nonetheless, mirabegron should be administered with caution to patients with clinically significant BOO [see Warnings and Precautions (5.2)].

Cardiac Electrophysiology

The effect of multiple doses of mirabegron 50 mg, 100 mg, and 200 mg (four times the maximum recommended dose) once daily on QTc interval was evaluated in a randomized, placebo- and active-controlled (moxifloxacin 400 mg), four-treatment arm, parallel crossover study in 352 healthy subjects. In a study with demonstrated ability to detect small effects, the upper bound of the one-sided 95% confidence interval for the largest placebo-adjusted, baseline-corrected QTc based on individual correction method (QTcI) was below 10 msec. For the 50 mg mirabegron dose group (the maximum approved dosage), the mean difference from placebo on QTcI interval at 4 to 5 hours post-dose was 3.7 msec (upper bound of the 95% CI 5.1 msec).

For the mirabegron 100 mg and 200 mg dose groups (dosages greater than the maximum approved dose and resulting in substantial multiples of the anticipated maximum blood levels at 50 mg), the mean differences from placebo in QTcI interval at 4 to 5 hours post dose were 6.1 msec (upper bound of the 95% CI 7.6 msec) and 8.1 msec (upper bound of the 95% CI 9.8 msec), respectively. At the mirabegron 200 mg dose, in females, the mean effect was 10.4 msec (upper bound of the 95% CI 13.4 msec).

In this thorough QT study, mirabegron increased heart rate on ECG in a dose-dependent manner. Maximum mean increases from baseline in heart rate for the 50 mg, 100 mg, and 200 mg dose groups compared to placebo were 6.7 bpm, 11 bpm, and 17 bpm, respectively. In the clinical efficacy and safety studies, the change from baseline in mean pulse rate for mirabegron 50 mg was approximately 1 bpm. In this thorough QT study, mirabegron also increased blood pressure in a dose-dependent manner (see Effects on Blood Pressure).

Effects on Blood Pressure

In a study of 352 healthy subjects assessing the effect of multiple daily doses of 50 mg, 100 mg, and 200 mg (four times the maximum recommended dose) of mirabegron for 10 days on the QTc interval, the maximum mean increase in supine systolic blood pressure (SBP)/diastolic blood pressure (DBP) at the maximum recommended dose of 50 mg was approximately 4.0/1.6 mm Hg greater than placebo [see Warnings and Precautions (5.1)]. The 24-hour average increases in SBP compared to placebo were 3.0, 5.5, and 9.7 mm Hg at mirabegron doses of 50 mg, 100 mg, and 200 mg, respectively. Increases in DBP were also dose-dependent, but were smaller than SBP.

In another study in 96 healthy subjects to assess the impact of age on pharmacokinetics of multiple daily doses of 50 mg, 100 mg, 200 mg, and 300 mg (six times the maximum recommended dose) of mirabegron for 10 days, SBP also increased in a dose-dependent manner. The mean maximum increases in SBP were approximately 2.5, 4.5, 5.5, and 6.5 mm Hg for mirabegron exposures associated with doses of 50 mg, 100 mg, 200 mg, and 300 mg, respectively.

In three, 12-week, double-blind, placebo-controlled, safety and efficacy studies (Studies 1, 2, and 3) in patients with OAB receiving mirabegron 25 mg, 50 mg, or 100 mg (two times the maximum recommended dose) once daily, mean increases in SBP/DBP compared to placebo of approximately 0.5 – 1 mm Hg were observed. Morning SBP increased by at least 15 mm Hg from baseline in 5.3%, 5.1%, and 6.7% of placebo, mirabegron 25 mg and mirabegron 50 mg patients, respectively. Morning DBP increased by at least 10 mm Hg in 4.6%, 4.1%, and 6.6% of placebo, mirabegron 25 mg, and mirabegron 50 mg patients, respectively. Both SBP and DBP increases were reversible upon discontinuation of treatment.

In a 12-week, double-blind, placebo-controlled, safety and efficacy study (Study 6) in patients with OAB receiving mirabegron 25 mg or 50 mg once daily coadministered with solifenacin succinate 5 mg, no consistent differences in 24‑hour mean SBP/DBP were observed compared to placebo, mirabegron or solifenacin succinate monotherapy as assessed with 24-hour Ambulatory Blood Pressure Monitoring (ABPM). Similar frequencies of categorical changes were observed for combination treatment versus placebo in 24‑hour mean SBP/DBP.

Effect on Intraocular Pressure (IOP)

Mirabegron 100 mg once daily did not increase IOP in healthy subjects after 56 days of treatment. In a phase 1 study assessing the effect of mirabegron on IOP using Goldmann applanation tonometry in 310 healthy subjects, a dose of mirabegron 100 mg was non-inferior to placebo for the primary endpoint of the treatment difference in mean change from baseline to day 56 in subject average IOP; the upper bound of the two-sided 95% CI of the treatment difference between mirabegron 100 mg and placebo was 0.3 mm Hg.

12.3 Pharmacokinetics

Absorption
MYRBETRIQ Monotherapy for Adult OAB
After oral administration of mirabegron in healthy volunteers, mirabegron was absorbed to reach maximum plasma concentrations (Cmax) at approximately 3.5 hours. The absolute bioavailability increased from 29% at a dose of 25 mg to 35% at a dose of 50 mg. Mean Cmax and AUC increased more than dose proportionally. This relationship was more apparent at doses above 50 mg. In the overall population of males and females, a 2-fold increase in dose from 50 mg to 100 mg mirabegron increased Cmax and AUCtau by approximately 2.9- and 2.6-fold, respectively, whereas a 4-fold increase in dose from 50 to 200 mg mirabegron increased Cmax and AUCtau by approximately 8.4- and 6.5-fold. Steady-state concentrations were achieved within 7 days of once daily dosing with mirabegron. After once daily administration, plasma exposure of mirabegron at steady-state was approximately double that seen after a single dose.

MYRBETRIQ/MYRBETRIQ Granules for Pediatric Neurogenic Detrusor Overactivity (NDO)
The median Tmax of mirabegron following oral administration of a single dose of MYRBETRIQ or mirabegron for extended-release oral suspension in pediatric patients under fed state was 4-5 hours. Population pharmacokinetic analysis predicted that the median Tmax of MYRBETRIQ or mirabegron for extended-release oral suspension at steady-state was 3-4 hours.

Effect of Food
  MYRBETRIQ Monotherapy for Adult OAB
  There were no clinically significant differences in mirabegron pharmacokinetics when administered with or without food in adult patients.
  MYRBETRIQ/MYRBETRIQ Granules for Pediatric Neurogenic Detrusor Overactivity (NDO)
  In the fasted state, steady-state mirabegron AUC increased by 120% relative to the fed state in pediatric patients
  receiving MYRBETRIQ. Fasted Cmax and AUC increased by 170% and 80%, respectively, compared to the fed state
  following administration of MYRBETRIQ Granules in healthy volunteers.

Distribution
MYRBETRIQ Monotherapy for Adult OAB
Mirabegron is extensively distributed in the body. The volume of distribution at steady-state (Vss) is approximately 1670 L following intravenous administration. Mirabegron is bound (approximately 71%) to human plasma proteins, and shows moderate affinity for albumin and alpha-1 acid glycoprotein. Mirabegron distributes to erythrocytes. Based on an in vitro study, erythrocyte concentrations of ^14C-mirabegron were about 2-fold higher than in plasma.

MYRBETRIQ/MYRBETRIQ Granules for Pediatric Neurogenic Detrusor Overactivity (NDO)

Mirabegron volume of distribution was relatively large in pediatric patients (the range of mean Vz/F under fed state in pediatric patients across studies: 4895-13726 L) and increased with increasing body weight.

Elimination

MYRBETRIQ Monotherapy for Adult OAB

The terminal elimination half-life (t1/2) of mirabegron is approximately 50 hours in patients.

MYRBETRIQ/MYRBETRIQ Granules for Pediatric Neurogenic Detrusor Overactivity (NDO)

The mean terminal elimination half-life (t1/2) of mirabegron is approximately 26 to 31 hours in pediatric patients.

Metabolism
  Mirabegron is metabolized via multiple pathways involving dealkylation, oxidation, (direct) glucuronidation, and amide hydrolysis. Mirabegron is the major circulating component following a single dose of ^14C-mirabegron. Two major metabolites were observed in human plasma and are phase 2 glucuronides representing 16% and 11% of total exposure, respectively. These metabolites are not pharmacologically active toward beta-3 adrenergic receptor. Although, in vitro studies suggest a role for CYP2D6 and CYP3A4 in the oxidative metabolism of mirabegron, in vivo results indicate that these isozymes play a limited role in the overall elimination. In healthy subjects who were genotypically poor metabolizers of CYP2D6, mean Cmax and AUCtau were approximately 16% and 17% higher than in extensive metabolizers of CYP2D6, respectively. In vitro and ex vivo studies have shown the involvement of butylcholinesterase, uridine diphospho-glucuronosyltransferases (UGT), and possibly alcohol dehydrogenase in the metabolism of mirabegron, in addition to CYP3A4 and CYP2D6.
  Excretion
  MYRBETRIQ Monotherapy for Adult OAB
  Total body clearance (CLtot) from plasma is approximately 57 L/h following intravenous administration. Renal clearance (CLR) is approximately 13 L/h, which corresponds to nearly 25% of CLtot. Renal elimination of mirabegron is primarily through active tubular secretion along with glomerular filtration. The urinary elimination of unchanged mirabegron is dose-dependent and ranges from approximately 6.0% after a daily dose of 25 mg to 12.2% after a daily dose of 100 mg. Following the administration of 160 mg ^14C-mirabegron solution to healthy volunteers, approximately 55% of the radioactivity dose was recovered in the urine and 34% in the feces. Approximately 25% of unchanged mirabegron was recovered in urine and 0% in feces.
  MYRBETRIQ/MYRBETRIQ Granules for Pediatric Neurogenic Detrusor Overactivity (NDO)
  Population pharmacokinetic model predicted that mirabegron clearance in pediatric patients increased with body weight.

Specific Populations

Geriatric Patients
  The Cmax and AUC of mirabegron following multiple oral doses in elderly volunteers (≥ 65 years) were similar to those in younger volunteers (18 to 45 years) [see Use in Specific Populations (8.5)].
  Pediatric Patients
  In patients 3 to less than 18 years of age, age was not predicted to affect mirabegron pharmacokinetic parameters after accounting for differences in body weight [see Use in Specific Populations (8.4)].
  Gender
  MYRBETRIQ Monotherapy for Adult OAB
  The Cmax and AUC of mirabegron were approximately 40% to 50% higher in females than in males. When corrected for differences in body weight, the mirabegron systemic exposure was 20%-30% higher in females compared to males.
  MYRBETRIQ/MYRBETRIQ Granules for Pediatric Neurogenic Detrusor Overactivity (NDO)
  Gender has no meaningful impact on mirabegron pharmacokinetics in the pediatric population from 3 to less than 18 years of age.
  Race
  The pharmacokinetics of mirabegron were comparable between Caucasians and African-American Blacks. Cross studies comparison showed that the exposure in Japanese subjects were higher than that in North American subjects. However, when the Cmax and AUC were normalized for dose and body weight, the difference was smaller.
  Patients with Renal Impairment
  Following single-dose administration of 100 mg mirabegron in adult volunteers with mild renal impairment (eGFR 60 to 89 mL/min/1.73 m^2 as estimated by MDRD), mean mirabegron Cmax and AUC were increased by 6% and 31% relative to adult volunteers with normal renal function. In adult volunteers with moderate renal impairment (eGFR 30 to 59 mL/min/1.73 m^2), Cmax and AUC were increased by 23% and 66%, respectively. In adult volunteers with severe renal impairment (eGFR 15 to 29 mL/min/1.73 m^2), mean Cmax and AUC values were 92% and 118% higher compared to healthy subjects with normal renal function. Mirabegron has not been studied in adult patients with End-Stage Renal Disease (ESRD) (eGFR less than 15 mL/min/1.73 m^2) or adult patients requiring dialysis.
  Patients with Hepatic Impairment
  Following single-dose administration of 100 mg mirabegron in adult volunteers with mild hepatic impairment (Child-Pugh Class A), mean mirabegron Cmax and AUC were increased by 9% and 19%, relative to adult volunteers with normal hepatic function. In adult volunteers with moderate hepatic impairment (Child-Pugh Class B), mean Cmax and AUC values were 175% and 65% higher. Mirabegron has not been studied in adult patients with severe hepatic impairment (Child-Pugh Class C).

Drug Interaction Studies

In Vitro Studies
  Effect of Other Drugs on Mirabegron
  Mirabegron is transported and metabolized through multiple pathways. Mirabegron is a substrate for CYP3A4, CYP2D6, butyrylcholinesterase, UGT, the efflux transporter P-glycoprotein (P-gp), and the influx organic cation transporters (OCT) OCT1, OCT2, and OCT3. Sulfonylurea hypoglycemic agents glibenclamide (a CYP3A4 substrate), gliclazide (a CYP2C9 and CYP3A4 substrate), and tolbutamide (a CYP2C9 substrate) did not affect the in vitro metabolism of mirabegron.
  Effect of Mirabegron on Other Drugs
  Studies of mirabegron using human liver microsomes and recombinant human CYP enzymes showed that mirabegron is a moderate and time-dependent inhibitor of CYP2D6 and a weak inhibitor of CYP3A. Mirabegron is unlikely to inhibit the metabolism of coadministered drugs metabolized by the following cytochrome P450 enzymes: CYP1A2, CYP2B6, CYP2C8, CYP2C9, CYP2C19, and CYP2E1 because mirabegron did not inhibit the activity of these enzymes at clinically relevant concentrations. Mirabegron did not induce CYP1A2 or CYP3A. Mirabegron inhibited P-gp-mediated drug transport at high concentrations. Mirabegron is predicted not to cause clinically relevant inhibition of OCT-mediated drug transport. Mirabegron did not affect the metabolism of glibenclamide or tolbutamide.
  Effect of Alcohol on Mirabegron
  The addition of alcohol (5, 10, 20, and 40%) increases the dissolution rate of mirabegron from MYRBETRIQ Granules at pH 6.8. The clinical impact on the systemic exposure of mirabegron has not been evaluated. The addition of alcohol does not increase the dissolution rate of MYRBETRIQ Granules at pH 1.0 or MYRBETRIQ (extended-release tablets) regardless of pH.
  In Vivo Studies
  MYRBETRIQ Monotherapy for Adult OAB
  The effect of coadministered drugs on the pharmacokinetics of mirabegron and the effect of mirabegron on the pharmacokinetics of coadministered drugs was studied after single and multiple doses of mirabegron. Most drug-drug interactions (DDI) were studied using mirabegron 100 mg extended-release tablets. However, interaction studies of mirabegron with metoprolol and with metformin were studied using mirabegron 160 mg immediate-release (IR) tablets.
  The effect of ketoconazole, rifampicin, solifenacin succinate, tamsulosin, and metformin on systemic mirabegron exposure is shown in Figure 1.
  The effect of mirabegron on metoprolol, desipramine, combined oral contraceptive-COC (ethinyl estradiol-EE, levonorgestrel-LNG), solifenacin succinate, digoxin, warfarin, tamsulosin, and metformin is shown in Figure 2.
  In these studies, the largest increase in mirabegron systemic exposure was seen in the ketoconazole DDI study. As a potent CYP3A4 inhibitor, ketoconazole increased mirabegron Cmax by 45% and mirabegron AUC by 80% after multiple dose administration of 400 mg of ketoconazole for 9 days prior to the administration of a single dose of 100 mg mirabegron in 23 male and female healthy subjects.
  As a moderate CYP2D6 inhibitor, mirabegron increased the systemic exposure to metoprolol and desipramine:
  • Mirabegron increased the Cmax of metoprolol by 90% and metoprolol AUC by 229% after multiple doses of 160 mg mirabegron IR tablets once daily for 5 days and a single dose of 100 mg metoprolol tablet in 12 healthy male subjects administered before and concomitantly with mirabegron.
  • Mirabegron increased the Cmax of desipramine by 79% and desipramine AUC by 241% after multiple dose administration of 100 mg mirabegron once daily for 18 days and a single dose of 50 mg desipramine before and concomitantly with mirabegron in 28 male and female healthy subjects.
  The effect on the pharmacokinetics of coadministered digoxin and tamsulosin was studied after multiple doses of a combination of mirabegron and solifenacin succinate. Concomitant administration of 0.25 mg digoxin with a combination of 5 mg solifenacin succinate and 50 mg mirabegron increased digoxin AUCtau and Cmax by approximately 10% and 14%, respectively. Concomitant administration of 0.4 mg tamsulosin with a combination of 5 mg solifenacin succinate and 50 mg mirabegron increased tamsulosin AUCtau and Cmax by 47.5% and 54.3%, respectively. The observed changes in the pharmacokinetics of tamsulosin are in line with cytochrome P450 inhibition as shown by coadministration with mirabegron alone.
  Figures 1 and 2 show the magnitude of these interactions on the pharmacokinetic parameters and the recommendations for dose adjustment, if any:

Figure 1: The Effect of Coadministered Drugs on Exposure of MYRBETRIQ and Dose Recommendation

(1) Although no dose adjustment is recommended with solifenacin succinate or tamsulosin based on the lack of pharmacokinetic interaction, MYRBETRIQ should be administered with caution to patients taking muscarinic antagonist medications for the treatment of OAB and in patients with clinically significant BOO because of the risk of urinary retention [see Warnings and Precautions (5.2)].

Figure 2: The Effect of MYRBETRIQ on Exposure of Coadministered Medication

(1) Since mirabegron is a moderate CYP2D6 inhibitor, the systemic exposure to CYP2D6 substrates such as metoprolol and desipramine is increased when coadministered with mirabegron. Therefore, appropriate monitoring and dose adjustment may be necessary, especially with narrow therapeutic index CYP2D6 substrates, such as thioridazine, flecainide, and propafenone [see Warnings and Precautions (5.4) and Drug Interactions (7.1)].
  (2) For patients who are initiating a combination of mirabegron and digoxin, the lowest dose for digoxin should initially be prescribed. Serum digoxin concentrations should be monitored and used for titration of the digoxin dose to obtain the desired clinical effect [see Drug Interactions (7.2)]. The same approach for the dose of digoxin should be followed when digoxin is coadministered with mirabegron and solifenacin succinate.
  (3) Warfarin was administered as a single 25 mg dose of the racemate (a mixture of R-warfarin and S-warfarin). Based on this single-dose study, mirabegron had no effect on the warfarin pharmacodynamic endpoints such as INR and prothrombin time. However, the effect of mirabegron on multiple doses of warfarin and on warfarin pharmacodynamic end points such as INR and prothrombin time has not been fully investigated [see Drug Interactions (7.3)].
  (4) Although no dose adjustment is recommended with solifenacin succinate or tamsulosin based on the lack of pharmacokinetic interaction, MYRBETRIQ should be administered with caution to patients taking muscarinic antagonist medications for the treatment of OAB and in BOO because of the risk of urinary retention [see Warnings and Precautions (5.2)].
  Based on the lack of relevant pharmacokinetic interaction, no dose adjustment for tamsulosin is recommended when coadministered with mirabegron and solifenacin succinate.

13 NONCLINICAL TOXICOLOGY

13.1 Carcinogenesis, Mutagenesis, Impairment of Fertility

Carcinogenicity

Long-term carcinogenicity studies were conducted in rats and mice dosed orally with mirabegron for two years. Male rats were dosed at 0, 12.5, 25, or 50 mg/kg/day and female rats and both sexes of mice were dosed at 0, 25, 50, or 100 mg/kg/day. Mirabegron showed no carcinogenic potential at systemic exposures (AUC) 38 to 45-fold higher than the MRHD in rats and 21 to 38-fold higher than the MRHD in mice than the human systemic exposure at the 50 mg dose.
Mutagenesis
Mirabegron was not mutagenic in the Ames bacterial reverse mutation assay, did not induce chromosomal aberrations in human peripheral blood lymphocytes at concentrations that were not cytotoxic, and was not clastogenic in the rat micronucleus assay.
Impairment of Fertility
Fertility studies in rats showed that mirabegron had no effect on either male or female fertility at non-lethal doses up to 100 mg/kg/day. Systemic exposures (AUC) at 100 mg/kg in female rats was estimated to be 22-fold the MRHD in women and 93-fold the MRHD in men.

14 CLINICAL STUDIES

14.1 MYRBETRIQ Monotherapy for Adult OAB

MYRBETRIQ was evaluated in three, 12-week, double-blind, randomized, placebo-controlled, parallel group, multicenter clinical trials in patients with overactive bladder with symptoms of urge urinary incontinence, urgency, and urinary frequency (Studies 1, 2, and 3). Entry criteria required that patients had symptoms of overactive bladder for at least 3 months duration, at least 8 micturitions per day, and at least 3 episodes of urgency with or without incontinence over a 3-day period. The majority of patients were Caucasian (94%) and female (72%) with a mean age of 59 years (range 18 – 95 years). The population included both naïve patients who had not received prior muscarinic antagonist pharmacotherapy for overactive bladder (48%) and those who had received prior muscarinic antagonist pharmacotherapy for OAB (52%).
In Study 1 (NCT00689104), patients were randomized to placebo, MYRBETRIQ 50 mg, MYRBETRIQ 100 mg, or an active control once daily. In Study 2 (NCT00662909), patients were randomized to placebo, MYRBETRIQ 50 mg or MYRBETRIQ 100 mg once daily. In Study 3 (NCT00912964), patients were randomized to placebo, MYRBETRIQ 25 mg or MYRBETRIQ 50 mg once daily.
The co-primary efficacy endpoints in all 3 trials were (1) change from baseline to end of treatment (Week 12) in mean number of incontinence episodes per 24 hours and (2) change from baseline to end of treatment (Week 12) in mean number of micturitions per 24 hours, based on a 3-day micturition diary. An important secondary endpoint was the change from baseline to end of treatment (Week 12) in mean volume voided per micturition.
Results for the co-primary endpoints and mean volume voided per micturition from Studies 1, 2, and 3 are shown in Table 13.

Table 13: Mean Baseline and Change from Baseline at Week 12 [Week 12 is the last observation on treatment.] for Incontinence Episodes, Micturition Frequency, and Volume Voided per Micturition in Patients with Overactive Bladder in Studies 1, 2, and 3
Parameter | Study 1 |  | Study 2 |  | Study 3
 | Placebo | MYRBETRIQ 50 mg | Placebo | MYRBETRIQ 50 mg | Placebo | MYRBETRIQ 25 mg | MYRBETRIQ 50 mg
Number of Incontinence Episodes per 24 Hours [For incontinence episodes per 24 hours, the analysis population is restricted to patients with at least 1 episode of incontinence at baseline.]
n | 291 | 293 | 325 | 312 | 262 | 254 | 257
Baseline (mean) | 2.67 | 2.83 | 3.03 | 2.77 | 2.43 | 2.65 | 2.51
Change from baseline (adjusted mean [Least squares mean adjusted for baseline, gender, and geographical region.]) | -1.17 | -1.57 | -1.13 | -1.47 | -0.96 | -1.36 | -1.38
Difference from placebo (adjusted mean) | -- | -0.41 | -- | -0.34 | -- | -0.40 | -0.42
95% Confidence Interval | -- | (-0.72, -0.09) | -- | (-0.66, -0.03) | -- | (-0.74, -0.06) | (-0.76, -0.08)
p-value | -- | 0.003 [Statistically significantly superior compared to placebo at the 0.05 level with multiplicity adjustment.] | -- | 0.026 | -- | 0.005 | 0.001
Number of Micturitions per 24 Hours
n | 480 | 473 | 433 | 425 | 415 | 410 | 426
Baseline (mean) | 11.71 | 11.65 | 11.51 | 11.80 | 11.48 | 11.68 | 11.66
Change from baseline (adjusted mean) | -1.34 | -1.93 | -1.05 | -1.66 | -1.18 | -1.65 | -1.60
Difference from placebo (adjusted mean) | -- | -0.60 | -- | -0.61 | -- | -0.47 | -0.42
95% Confidence Interval | -- | (-0.90, -0.29) | -- | (-0.98, -0.24) | -- | (-0.82, -0.13) | (-0.76, -0.08)
p-value | -- | < 0.001 | -- | 0.001 | -- | 0.007 | 0.015
Volume Voided (mL) per Micturition
n | 480 | 472 | 433 | 424 | 415 | 410 | 426
Baseline (mean) | 156.7 | 161.1 | 157.5 | 156.3 | 164.0 | 165.2 | 159.3
Change from baseline (adjusted mean) | 12.3 | 24.2 | 7.0 | 18.2 | 8.3 | 12.8 | 20.7
Difference from placebo (adjusted mean) | -- | 11.9 | -- | 11.1 | -- | 4.6 | 12.4
95% Confidence Interval | -- | (6.3, 17.4) | -- | (4.4, 17.9) | -- | (-1.6, 10.8) | (6.3, 18.6)
p-value | -- | < 0.001 | -- | 0.001 | -- | 0.15 | < 0.001

MYRBETRIQ 25 mg was effective in treating the symptoms of OAB within 8 weeks and MYRBETRIQ 50 mg was effective in treating the symptoms of OAB within 4 weeks. Efficacy of both 25 mg and 50 mg doses of MYRBETRIQ was maintained through the 12-week treatment period.

Figures 3 through 8 show the co-primary endpoints, mean change from baseline (BL) over time in number of incontinence episodes per 24 hours, and mean change from baseline over time in number of micturitions per 24 hours, in Studies 1, 2, and 3.

Figure 3: Mean (SE) Change from Baseline in Mean Number of Incontinence Episodes per 24 Hours – Study 1
Figure 4: Mean (SE) Change from Baseline in Mean Number of Micturitions per 24 Hours – Study 1
Figure 5: Mean (SE) Change from Baseline in Mean Number of Incontinence Episodes per 24 Hours – Study 2
Figure 6: Mean (SE) Change from Baseline in Mean Number of Micturitions per 24 Hours – Study 2
Figure 7: Mean (SE) Change from Baseline in Mean Number of Incontinence Episodes per 24 Hours – Study 3
Figure 8: Mean (SE) Change from Baseline in Mean Number of Micturitions per 24 Hours – Study 3

14.2 MYRBETRIQ Combination Therapy for Adult OAB

Coadministration of MYRBETRIQ with Solifenacin Succinate

Coadministration of MYRBETRIQ with solifenacin succinate was evaluated in a 12-week, double-blind, randomized, placebo-controlled, parallel group, multicenter clinical trial in patients with OAB with symptoms of urge urinary incontinence, urgency, and urinary frequency (Study 6). Entry criteria required that patients had symptoms of OAB for at least 3 months duration, on average at least 8 micturitions and at least 1 urgency episode per day, and at least 3 episodes of incontinence, over a 7-day period. The majority of patients were Caucasian (80%) and female (77%) with a mean age of 57 years (range 18 to 86 years). The population included both naïve patients who had not received prior pharmacotherapy for OAB (54%) and those who had received prior pharmacotherapy for OAB (46%).

In Study 6 (NCT01972841), patients were randomized to placebo, solifenacin succinate 5 mg, MYRBETRIQ 25 mg, MYRBETRIQ 50 mg, solifenacin succinate 5 mg plus MYRBETRIQ 25 mg, or solifenacin succinate 5 mg plus MYRBETRIQ 50 mg once daily.

The co-primary efficacy endpoints in Study 6 were (1) change from baseline to end of treatment (week 12) in mean number of incontinence episodes per 24 hours and (2) change from baseline to end of treatment (week 12) in mean number of micturitions per 24 hours, based on a 7-day micturition diary. An important secondary endpoint was the change from baseline to end of treatment (week 12) in mean volume voided per micturition.

Results for the co-primary endpoints and mean volume voided per micturition for the overall patient population from Study 6 are shown in Table 14.

Table 14: Mean Baseline and Change from Baseline at Week 12 [Week 12 is the last observation on treatment.] for Incontinence Episodes, Micturition Frequency, and Volume Voided per Micturition Overall Population with Overactive Bladder in Study 6
Parameter | Placebo | MYRBETRIQ; 25 mg | MYRBETRIQ; 50 mg | Solifenacin Succinate; 5 mg | MYRBETRIQ 25 mg; +; Solifenacin Succinate 5 mg | MYRBETRIQ 50 mg; +; Solifenacin Succinate 5 mg
Number of Incontinence Episodes per 24 Hours
n | 412 | 409 | 406 | 413 | 823 | 816
Baseline (mean) | 3.40 | 3.42 | 3.16 | 3.59 | 3.21 | 3.15
Change from baseline; (adjusted mean [Least squares mean adjusted for baseline, gender, age group (< 65, ≥ 65 years), previous OAB medication (yes, no), and geographical region using an ANCOVA model.]) | -1.34 | -1.70 | -1.76 | -1.79 | -2.04 | -1.98
Difference from; Solifenacin Succinate; (adjusted mean) | -- | -- | -- | -- | -0.25 | -0.20
95% Confidence Interval | -- | -- | -- | -- | (-0.49, -0.01) | (-0.44, 0.04)
Difference from; MYRBETRIQ; (at the same MYRBETRIQ dose, adjusted mean) | -- | -- | -- | -- | -0.34 | -0.23
95% Confidence Interval | -- | -- | -- | -- | (-0.58, -0.10) | (-0.47, 0.01)
Number of Micturitions per 24 Hours
n | 412 | 409 | 406 | 413 | 823 | 816
Baseline (mean) | 10.97 | 10.81 | 11.19 | 10.74 | 10.72 | 10.72
Change from baseline; (adjusted mean) | -1.64 | -2.00 | -2.03 | -2.20 | -2.49 | -2.59
Difference from; Solifenacin Succinate; (adjusted mean) | -- | -- | -- | -- | -0.29 | -0.39
95% Confidence Interval | -- | -- | -- | -- | (-0.57, -0.01) | (-0.67, -0.11)
Difference from; MYRBETRIQ; (at the same MYRBETRIQ dose, adjusted mean) | -- | -- | -- | -- | -0.48 | -0.56
95% Confidence Interval | -- | -- | -- | -- | (-0.76, -0.21) | (-0.84, -0.28)
Volume Voided (mL) per Micturition
n | 413 | 407 | 408 | 411 | 821 | 821
Baseline (mean) | 157.82 | 152.46 | 155.35 | 151.86 | 159.19 | 153.83
Change from baseline; (adjusted mean) | 8.44 | 13.32 | 21.99 | 30.99 | 34.84 | 39.73
Difference from; Solifenacin Succinate; (adjusted mean) | -- | -- | -- | -- | 3.85 | 8.75
95% Confidence Interval | -- | -- | -- | -- | (-2.29, 10.00) | (2.61, 14.89)
Difference from; MYRBETRIQ; (at the same MYRBETRIQ dose, adjusted mean) | -- | -- | -- | -- | 21.52 | 17.74
95% Confidence Interval | -- | -- | -- | -- | (15.35, 27.68) | (11.58, 23.90)
ANCOVA: Analysis of covariance

Figures 9 and 10 show the co-primary endpoints, mean change from baseline (BL) over time in number of incontinence episodes per 24 hours, and mean change from baseline over time in number of micturitions per 24 hours, in the overall patient population in Study 6.

Figure 9: Mean Change from Baseline in Mean (± SE) Number of Incontinence Episodes per 24 Hours at Each Visit (FAS) – Study 6
Figure 10: Mean Change from Baseline in Mean (± SE) Number of Micturitions per 24 Hours at Each Visit (FAS) – Study 6

MYRBETRIQ as Add-on Therapy to Solifenacin Succinate

MYRBETRIQ add-on therapy to solifenacin succinate was evaluated in one, 12-week, double-blind, randomized, active‑controlled, multicenter clinical trial in incontinent OAB patients who received solifenacin succinate for 4 weeks and required additional relief for their OAB symptoms (Study 7). Entry criteria required that patients had symptoms of OAB for at least 3 months duration (urge urinary incontinence, urgency, and urinary frequency), and at least 1 incontinence episode during a 3-day period after being treated with solifenacin succinate 5 mg for 4 weeks. The majority of patients were Caucasian (94%) and female (83%) with a mean age of 57 years (range 18 to 89 years). Patients were randomized to solifenacin succinate 5 mg, solifenacin succinate 10 mg, or solifenacin succinate 5 mg plus MYRBETRIQ 25 mg once daily. After 4 weeks, all patients in the combination treatment arm had a dose increase from MYRBETRIQ 25 mg to MYRBETRIQ 50 mg.

The primary efficacy endpoint in Study 7 (NCT01908829) was change from baseline to end of treatment (week 12) in mean number of incontinence episodes per 24 hours. Two important secondary endpoints were change from baseline to end of treatment in mean number of micturitions per 24 hours and change from baseline to end of treatment in mean volume voided per micturition. Results for the primary and additional endpoints from Study 7 are shown in Table 15.

Table 15: Change from Baseline at Week 12 [Week 12 is the last observation on treatment.] for Incontinence Episodes, Micturition Frequency, and Volume Voided per Micturition in Patients with Overactive Bladder in Study 7
Parameter | Solifenacin Succinate; 5 mg | MYRBETRIQ; 25 mg/50 mg; +; Solifenacin; Succinate; 5 mg
Number of Incontinence Episodes per 24 Hours
n | 704 | 706
Baseline (mean) | 3.15 | 3.24
Change from baseline (adjusted mean [Least squares mean adjusted for baseline, gender, age group (< 65, ≥ 65 years), geographical region, and 4-week incontinence reduction group using ANCOVA model.]) | -1.53 | -1.80
Difference (MYRBETRIQ + Solifenacin Succinate) from Solifenacin Succinate (adjusted mean [Differences of adjusted means are calculated by subtracting the adjusted mean of solifenacin succinate monotherapy groups from adjusted mean of MYRBETRIQ + Solifenacin Succinate group based on ANCOVA model described above.]) | -0.26 | --
95% Confidence Interval | (-0.47, -0.05) | --
Number of Micturitions per 24 Hours
n | 704 | 706
Baseline (mean) | 8.90 | 9.13
Change from baseline (adjusted mean) | -1.14 | -1.59
Difference (MYRBETRIQ + Solifenacin Succinate) from Solifenacin Succinate (adjusted mean) | -0.45 (0.12) | --
95% Confidence Interval | (-0.67, -0.22) | --
Volume Voided (mL) per Micturition
n | 682 | 680
Baseline (mean) | 170.92 | 172.93
Change from baseline (adjusted mean) | 16.52 | 28.05
Difference (MYRBETRIQ + Solifenacin Succinate) from Solifenacin Succinate (adjusted mean) | 11.52 | --
95% Confidence Interval | (6.06, 16.99)
ANCOVA: Analysis of covariance

Long-term Coadministration of MYRBETRIQ with Solifenacin Succinate

Long-term efficacy of coadministration of MYRBETRIQ 50 mg with solifenacin succinate 5 mg was evaluated in a 52-week, double-blind, randomized, active-controlled, parallel group, multicenter clinical trial in patients with OAB Study 8 (NCT02045862). The primary objective of this study was to evaluate the safety and tolerability of long-term combination treatment and the evaluation of efficacy was the secondary objective of the study. Entry criteria included patients who had completed Study 6 or Study 7 or new patients. All patients had symptoms of OAB for at least 3 months duration, on average at least 8 micturitions and at least 1 urgency episode per day, and at least 3 episodes of incontinence over a 7-day period. Patients were randomized to solifenacin succinate 5 mg, MYRBETRIQ 50 mg, or solifenacin succinate 5 mg plus MYRBETRIQ 50 mg once daily.

Primary efficacy variables were change from baseline to end of treatment in mean number of incontinence episodes per 24 hours and change from baseline to end of treatment in mean number of micturitions per 24 hours. Combination treatment with MYRBETRIQ and solifenacin succinate demonstrated statistically significant greater improvements from baseline compared to MYRBETRIQ 50 mg and solifenacin succinate 5 mg for both efficacy endpoints. The improvements from baseline observed with coadministration of MYRBETRIQ 50 mg and solifenacin succinate 5 mg compared to MYRBETRIQ 50 mg and solifenacin succinate 5 mg were demonstrated at 3 months and were maintained throughout the 1‑year treatment period. Also, for the secondary efficacy variable of change from baseline to end of treatment in mean volume voided (MVV) per micturition, the increase in MVV was statistically significantly greater for combination treatment compared to the MYRBETRIQ 50 mg and solifenacin succinate 5 mg groups.

14.3 MYRBETRIQ/MYRBETRIQ Granules for Pediatric Neurogenic Detrusor Overactivity (NDO)

The efficacy of MYRBETRIQ/MYRBETRIQ Granules was evaluated in Study 9 (NCT02751931), a 52-week, open-label, baseline-controlled, multicenter, dose titration study in pediatric patients 3 years of age and older for the treatment of neurogenic detrusor overactivity (NDO). Study 9 included patients 3 to 17 years of age. Entry criteria required that patients had a diagnosis of neurogenic detrusor overactivity (NDO) with involuntary detrusor contractions with detrusor pressure increase greater than 15 cm H2O and that patients or their caregivers practiced clean intermittent catheterization (CIC). MYRBETRIQ/MYRBETRIQ Granules were administered orally once daily. All patients initially received a weight-based starting dose equivalent to 25 mg daily dose followed by dose titration to a dose equivalent of 50 mg daily dose. The duration of the dose titration period was up to 8 weeks and this period was followed by a dose maintenance period that continued for the duration of the 52-week study.

In Study 9, a total of 86 patients 3 to 17 years of age received MYRBETRIQ/MYRBETRIQ Granules. Of these, 71 patients completed treatment through week 24 and 70 completed 52 weeks of treatment. A total of 68 patients (43 patients 3 to less than 12 years of age and 25 patients 12 to 17 years of age) had valid urodynamic measurements for evaluation of efficacy. The study population included 39 males (45%) and 47 females (55%). The optimized maintenance dose within this study population included 94% of patients at the maximum dose, and 6% of patients at the starting dose.

The primary efficacy endpoint was change from baseline in the patients’ maximum cystometric (bladder) capacity (MCC) after 24 weeks of treatment with MYRBETRIQ/MYRBETRIQ Granules. As shown in Table 16, improvements in MCC were observed in patients 3 to less than 12 years of age and in patients 12 to 17 years of age. The magnitude of the observed changes from baseline in the primary and secondary efficacy endpoints were comparable between patients 3 to less than 12 years of age and patients 12 to 17 years of age.

Table 16: Change from Baseline in Maximum Cystometric Capacity (MCC) at 24 Weeks in Pediatric Patients with Neurogenic Detrusor Overactivity (NDO) Treated with MYRBETRIQ/MYRBETRIQ Granules in Study 9
Parameter |  | Children; Aged 3 to Less than 12 Years; (N=43) [N is the number of patients who took at least one dose and provided valid values for MCC at Baseline and Week 24.]; Mean (SD) | Adolescents; Aged 12 to 17 Years; (N=25); Mean (SD)
Maximum Cystometric Capacity (mL)
 | Baseline; Week 24; Change from baseline; 95% CI | 159 (95); 231 (129); 72 (87); (45, 99) | 239 (99); 352 (125); 113 (83); (79, 147)

Secondary efficacy endpoints from Study 9 for MYRBETRIQ/MYRBETRIQ Granules in pediatric patients with neurogenic detrusor overactivity (NDO) are shown below in Table 17 and Table 18.

Table 17: Changes from Baseline in Other Urodynamic Parameters at Week 24 in Pediatric Patients with Neurogenic Detrusor Overactivity (NDO) Treated with MYRBETRIQ/MYRBETRIQ Granules in Study 9
Parameter | Children; Aged 3 to Less than 12 Years; (N=43) [N is the number of patients who took at least one dose and provided valid values for MCC at Baseline and Week 24.]; Mean (SD) | Adolescents; Aged 12 to 17 Years; (N=25); Mean (SD)
Bladder Compliance (mL/cm H2O) [Number of patients (Children/Adolescents) with data available for both Baseline and Week 24; Bladder Compliance: n=33/21; Number of Overactive Detrusor Contractions: n=36/22; Bladder Volume Prior To First Detrusor Contraction: n=38/24.]
Baseline Change from baseline
Baseline Change from baseline | 16.0 (55.8); 14.6 (42.1); 95% CI: -0.3, 29.5 | 11.1 (10.7); 13.6 (15.0); 95% CI: 6.7, 20.4
Number of Overactive Detrusor Contractions (> 15 cm H2O)
Baseline Change from baseline
Baseline Change from baseline | 3.0 (4.0); -1.9 (4.2); 95% CI: -3.3, -0.4 | 2.1 (3.1); -0.8 (3.9); 95% CI: -2.5, 0.9
Bladder Volume Prior To First Detrusor Contraction (> 15 cm H2O)
Baseline Change from baseline | 115 (83); 93 (88); 95% CI: 64, 122 | 177 (117); 121 (160); 95% CI: 54, 189

Table 18: Changes from Baseline in Maximum Catheterized Urine Volume and Number of Leakage Episodes at Week 24 in Pediatric Patients with Neurogenic Detrusor Overactivity (NDO) Treated with MYRBETRIQ/MYRBETRIQ Granules in Study 9
Parameter | Children; Aged 3 to Less than 12 Years; (N=43) [N is the number of patients who took at least one dose and provided valid values for MCC at Baseline and Week 24.]; Mean (SD) | Adolescents; Aged 12 to 17 Years; (N=25); Mean (SD)
Maximum Catheterized Urine Volume per Day (mL) [Number of patients (Children/Adolescents) with data available for both Baseline and Week 24; Maximum Catheterized Urine Volume per Day: n=41/23; Number of Leakage Episodes per Day: n=26/21.]
Baseline Change from baseline
Baseline Change from baseline | 304 (109); 50 (104); 95% CI: 17, 83 | 360 (111); 84 (122); 95% CI: 32, 137
Number of Leakage Episodes per Day
Baseline Change from baseline | 2.8 (3.7); -2.0 (3.2); 95% CI: -3.2, -0.7 | 1.8 (1.7); -1.0 (1.1); 95% CI: -1.5, -0.5

16 HOW SUPPLIED/STORAGE AND HANDLING

16.1 MYRBETRIQ (mirabegron extended-release tablets)

MYRBETRIQ is supplied as oval, film-coated, extended-release tablets, available in bottles as follows:

Strength | 25 mg | 50 mg
Shape/Color | Oval/Brown | Oval/Yellow
Branding on Tablet | logo, 325 | logo, 355
Available | bottles of approximately 960 tablets, NDC 55154-8712-8 | bottles of approximately 1080 tablet, NDC 55154-8713-8

Store and Dispense
Store at 20°C to 25°C (68°F to 77°F) with excursions permitted from 15°C to 30°C (59°F to 86°F) [see USP Controlled Room Temperature].

17 PATIENT COUNSELING INFORMATION

Advise the patient and/or caregiver to read the FDA-approved patient labeling (Patient Information).

Increases in Blood Pressure

Inform patients and/or their caregivers that MYRBETRIQ/MYRBETRIQ Granules may increase blood pressure. Advise patients, especially patients with hypertension, to periodically monitor their blood pressure and report increased measurement to their health care provider [see Warnings and Precautions (5.1)].

Urinary Retention

Inform patients and/or their caregivers that MYRBETRIQ may cause urinary retention in adult patients with bladder outlet obstruction and in patients taking muscarinic antagonist medications for the treatment of OAB. Advise patients to contact their physician if they experience these effects while taking MYRBETRIQ [see Warnings and Precautions (5.2)].

Angioedema

Inform patients and/or their caregivers that MYRBETRIQ/MYRBETRIQ Granules may cause angioedema. Advise patients and/or their caregivers to promptly discontinue MYRBETRIQ/MYRBETRIQ Granules and seek medical attention if angioedema associated with the upper airway swelling occurs as this may be life-threatening [see Warnings and Precautions (5.3)].

Drug Interactions

Advise patients to report their use of any other prescription or nonprescription medications or dietary supplements because co-administration with MYRBETRIQ/MYRBETRIQ Granules may require a dose adjustment and/or increased monitoring of these drugs [see Drug Interactions (7)].

Administration Instructions

MYRBETRIQ

Advise adult patients to swallow MYRBETRIQ whole with water and not to chew, divide, or crush. Advise adult patients to take MYRBETRIQ with or without food.

Advise pediatric patients and/or their caregivers to swallow MYRBETRIQ whole with water and not to chew, divide, or crush. Advise pediatric patients to take MYRBETRIQ with food.

MYRBETRIQ Granules

Advise pediatric patients and/or their caregivers to use an appropriate measuring device and instructions for measuring the correct dose of MYRBETRIQ Granules for extended-release oral suspension. Instruct patients or their caregivers that patients should take MYRBETRIQ Granules for extended-release oral suspension orally within 1 hour after preparation with food once daily and not save the dose for later.

The bottle should be shaken for 1 minute each day if the suspension will not be used for 2 or more days. When ready to use, shake the bottle vigorously for 1 minute then let it stand until the foam on top of the suspension is gone (approximately 1 to 2 minutes).

Missed Dose

Instruct patients and/or their caregivers to take any missed doses as soon as they remember, unless more than 12 hours have passed since the missed dose. If more than 12 hours have passed, the missed dose can be skipped and the next dose should be taken at the usual time.

Marketed and Distributed by:
Astellas Pharma US, Inc.
Northbrook, IL 60062

Distributed By:

Cardinal Health

Dublin, OH 43017

ER7606J Rev. A

ER7607J Rev. A

MYRBETRIQ is a registered trademark of Astellas Pharma Inc. All other trademarks are the property of their respective owners.

© 2012 – 2021 Astellas Pharma US, Inc.

Patient Information

MYRBETRIQ® (meer-BEH-trick)

(mirabegron extended-release tablets) for oral use

MYRBETRIQ® (meer-BEH-trick) GRANULES

(mirabegron for extended-release oral suspension)

What are MYRBETRIQ tablets and MYRBETRIQ GRANULES?

Adults

- MYRBETRIQ tablets is a prescription medicine that can be used alone or with solifenacin succinate to treat adults with the following symptoms due to a condition called overactive bladder (OAB):
  - Urge urinary incontinence: a strong need to urinate with leaking or wetting accidents
  - Urgency: a strong need to urinate right away
  - Frequency: urinating often

Children

- MYRBETRIQ tablets is a prescription medicine used to treat children 3 years of age and older weighing at least 77 pounds (35 kg), with a condition called neurogenic detrusor overactivity (NDO).
- MYRBETRIQ GRANULES is a prescription medicine used to treat children 3 years of age and older with a condition called neurogenic detrusor overactivity (NDO).

It is not known if MYRBETRIQ tablets and MYRBETRIQ GRANULES to treat NDO, are safe and effective in children under 3 years of age.

Who should not take MYRBETRIQ tablets or MYRBETRIQ GRANULES?

Do not take MYRBETRIQ tablets or MYRBETRIQ GRANULES if you are allergic to mirabegron or any of the ingredients in MYRBETRIQ tablets or MYRBETRIQ GRANULES. See the end of this Patient Information leaflet for a complete list of ingredients in MYRBETRIQ tablets and MYRBETRIQ GRANULES.

Before you take MYRBETRIQ tablets or MYRBETRIQ GRANULES, tell your doctor about all of your medical conditions, including if you:

- have liver problems.
- have kidney problems.
- have very high uncontrolled blood pressure.
- have trouble emptying your bladder or you have a weak urine stream.
- are pregnant or plan to become pregnant. It is not known if MYRBETRIQ tablets or MYRBETRIQ GRANULES will harm your unborn baby. Talk to your doctor if you are pregnant or plan to become pregnant.
- are breastfeeding or plan to breastfeed. It is not known if MYRBETRIQ tablets or MYRBETRIQ GRANULES passes into your breast milk. Talk to your doctor about the best way to feed your baby if you take MYRBETRIQ tablets or MYRBETRIQ GRANULES.

Tell your doctor about all the medicines you take, including prescription and over-the-counter medicines, vitamins, and herbal supplements. MYRBETRIQ tablets and MYRBETRIQ GRANULES may affect the way other medicines work, and other medicines may affect how MYRBETRIQ tablets and MYRBETRIQ GRANULES work.

Especially tell your doctor if you take:

- thioridazine (Mellaril or Mellaril-S)
- flecainide (Tambocor)
- propafenone (Rythmol)
- digoxin (Lanoxin)
- solifenacin succinate (VESIcare)

How should I take MYRBETRIQ tablets?

- Take MYRBETRIQ tablets exactly as your doctor tells you to take it.
- You should take 1 MYRBETRIQ tablet 1 time a day.
- If your doctor prescribes MYRBETRIQ tablets and solifenacin succinate together, you should take 1 MYRBETRIQ tablet and 1 solifenacin succinate tablet at the same time, 1 time a day.
- You should take MYRBETRIQ tablets with water and swallow the tablet whole.
- Do not chew, break, or crush the tablet.
- Adults can take MYRBETRIQ tablets with or without food.
- Adults can take MYRBETRIQ tablets and solifenacin succinate together with or without food.
- Children should take MYRBETRIQ tablets with food.
- If you miss a dose of MYRBETRIQ tablets, take it as soon as possible. If it has been more than 12 hours since taking the last dose of MYRBETRIQ tablets, skip that dose and take the next dose at the usual time.
- If you take too much MYRBETRIQ tablets, call your doctor or go to the nearest hospital emergency room right away.

How should I take MYRBETRIQ GRANULES?

- You or your child should take MYRBETRIQ GRANULES exactly as the doctor tells you to take it.
- You or your child should take MYRBETRIQ GRANULES by mouth 1 time a day.
- You or your child should take MYRBETRIQ GRANULES with food.
- You or your child should take MYRBETRIQ GRANULES immediately after preparation (see the steps below). Do not save the dose for later use.
- If you or your child misses a dose of MYRBETRIQ GRANULES, take or give it as soon as possible. If it has been more than 12 hours since the last dose of MYRBETRIQ GRANULES, skip that dose and take or give the next dose at the usual time.
- If you or your child takes too much MYRBETRIQ GRANULES, call your doctor or go to the nearest hospital emergency room right away.

Note: You will receive MYRBETRIQ GRANULES from the pharmacy as a suspension. The suspension is prepared by your pharmacist. You will receive an oral dosing device with the suspension. If the suspension will not be used for 2 or more days, shake the bottle vigorously for 1 minute each day to make sure the granules are mixed well (dispersed). Talk to your pharmacist if you have any questions.
Steps to prepare and take the suspension:
Step 1. Shake the bottle vigorously for 1 minute then let it stand until the foam on top of the suspension is gone (approximately 1 to 2 minutes). If the granules have not mixed well (dispersed), shake the bottle vigorously again for 1 minute and let it stand until the foam is gone.
Step 2. Using the oral dosing device provided by the pharmacist, place the dose into the oral dosing device and take the suspension within 1 hour with food. Disregard any bubbles.
Step 3. After each use, wash the oral dosing device with mild household detergent, rinse under running tap water, and allow it to air dry.

What are the possible side effects of MYRBETRIQ tablets and MYRBETRIQ GRANULES?

MYRBETRIQ tablets and MYRBETRIQ GRANULES may cause serious side effects, including:

- increased blood pressure. MYRBETRIQ tablets and MYRBETRIQ GRANULES may cause your blood pressure to increase or make your blood pressure worse if you have a history of high blood pressure. You and your doctor should check your blood pressure while you are taking MYRBETRIQ tablets or MYRBETRIQ GRANULES. Call your doctor if you have increased blood pressure.
- inability to empty your bladder (urinary retention). MYRBETRIQ tablets may increase your chances of not being able to empty your bladder if you have bladder outlet obstruction or if you are taking other medicines to treat overactive bladder. Tell your doctor right away if you are unable to empty your bladder.
- angioedema. MYRBETRIQ tablets and MYRBETRIQ GRANULES may cause an allergic reaction with swelling of the lips, face, tongue, or throat with or without difficulty breathing. Stop using MYRBETRIQ tablets or MYRBETRIQ GRANULES and go to the nearest hospital emergency room right away.

Adults with Overactive Bladder

The most common side effects of MYRBETRIQ tablets include:

- high blood pressure
- pain or swelling of the nose or throat (nasopharyngitis)
- urinary tract infection
- headache

The most common side effects of MYRBETRIQ tablets, when used with solifenacin succinate, include:

- dry mouth
- urinary tract infection
- constipation
- fast heartbeat

Children with Neurogenic Detrusor Overactivity

The most common side effects of MYRBETRIQ tablets and MYRBETRIQ GRANULES include:

- urinary tract infection
- pain or swelling of the nose or throat (nasopharyngitis)
- constipation
- headache

Tell your doctor if you have any side effect that bothers you, does not go away, or if you have swelling of the face, lips, tongue or throat, hives, skin rash or itching while taking MYRBETRIQ tablets or MYRBETRIQ GRANULES.

These are not all the possible side effects of MYRBETRIQ tablets and MYRBETRIQ GRANULES. For more information, ask your doctor or pharmacist.

Call your doctor for medical advice about side effects. You may report side effects to FDA at 1-800-FDA-1088.

How should I store MYRBETRIQ tablets or MYRBETRIQ GRANULES?

- Store MYRBETRIQ tablets at room temperature between 68°F to 77°F (20°C to 25°C). Keep the bottle closed. Throw away (discard) medicine that is out of date or no longer needed.
- Store MYRBETRIQ GRANULES at room temperature between 68°F to 77°F (20°C to 25°C). Use MYRBETRIQ GRANULES within 28 days (4 weeks) after the date the pharmacist prepares the suspension. The pharmacist will write the expiration date on the bottle. Throw away (discard) any unused medicine after the expiration date.

Keep MYRBETRIQ tablets, MYRBETRIQ GRANULES, and all medicines out of the reach of children.

General information about the safe and effective use of MYRBETRIQ tablets and MYRBETRIQ GRANULES.

Medicines are sometimes prescribed for purposes other than those listed in a Patient Information leaflet. Do not use MYRBETRIQ tablets or MYRBETRIQ GRANULES for a condition for which it was not prescribed. Do not give MYRBETRIQ tablets or MYRBETRIQ GRANULES to other people, even if they have the same symptoms you have. It may harm them.

This leaflet summarizes the most important information about MYRBETRIQ tablets and MYRBETRIQ GRANULES. If you would like more information, talk with your doctor. You can ask your doctor or pharmacist for information about MYRBETRIQ tablets or MYRBETRIQ GRANULES that is written for health professionals.

What are the ingredients in MYRBETRIQ tablets?

Active ingredient: mirabegron

Inactive ingredients: butylated hydroxytoluene, hydroxypropyl cellulose, hypromellose, magnesium stearate, polyethylene glycol, polyethylene oxide, red ferric oxide (25 mg MYRBETRIQ tablet only), and yellow ferric oxide.

What are the ingredients in MYRBETRIQ GRANULES?

Active ingredient: mirabegron

Inactive ingredients: acesulfame potassium, diluted hydrochloric acid, ethylparaben, hypromellose, magnesium stearate, mannitol, methylparaben, silicon dioxide, simethicone, sodium polystyrene sulfonate, and xanthan gum.

Marketed and Distributed by:

Astellas Pharma US, Inc.

Northbrook, IL 60062

MYRBETRIQ and VESIcare are registered trademarks of Astellas Pharma Inc.

All other trademarks are the property of their respective owners.

© 2012 – 2021 Astellas Pharma US, Inc.

For more information, go to www.Myrbetriq.com or call 1-800-727-7003.

Distributed By:

Cardinal Health

Dublin, OH 43017

ER7606J Rev. A

ER7607J Rev. A

This Patient Information has been approved by the U.S. Food and Drug Administration. Revised: 4/2021

Package/Label Display Panel

Contains Approximately

960 Tablets

MYRBETRIQ®

(mirabegron) extended release

tablets

25 mg

ONCE-DAILY

Each tablet contains:

25 mg of mirabegron.

Pharmacist: Dispense in a tight

container as defined in USP.

Rx Only

WARNING: Keep out of reach of

Children.

Package/Label Display Panel

Contains Approximately

100 Tablets

MYRBETRIQ®

(mirabegron) extended release tablets

50 mg

ONCE-DAILY

Each tablet contains:

50 mg of mirabegron.

Pharmacist: Dispense in a tight

container as defined in USP.

Rx Only

WARNING: Keep out of reach of

Children.